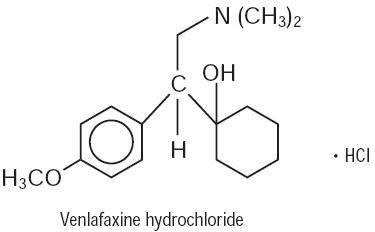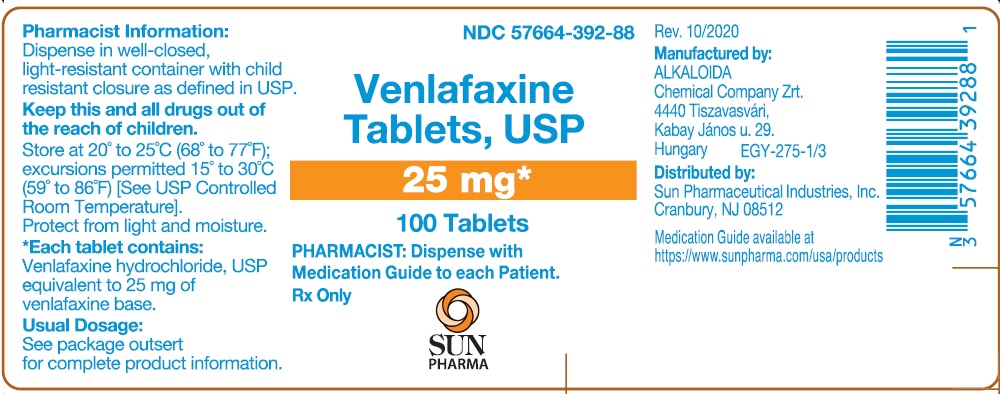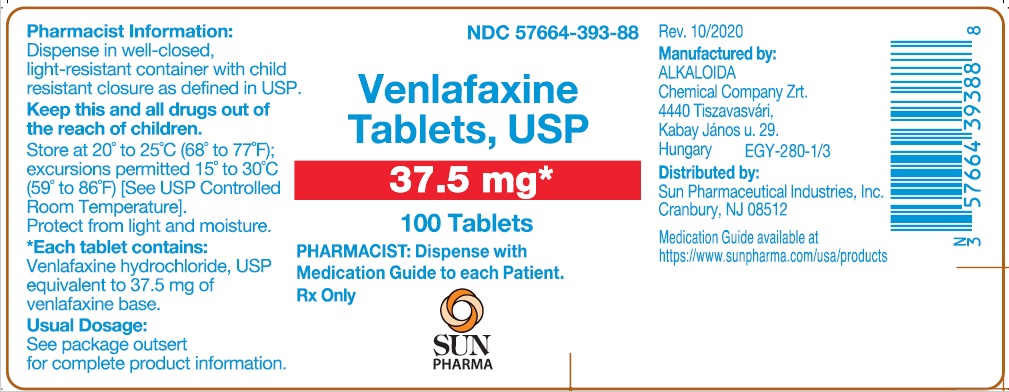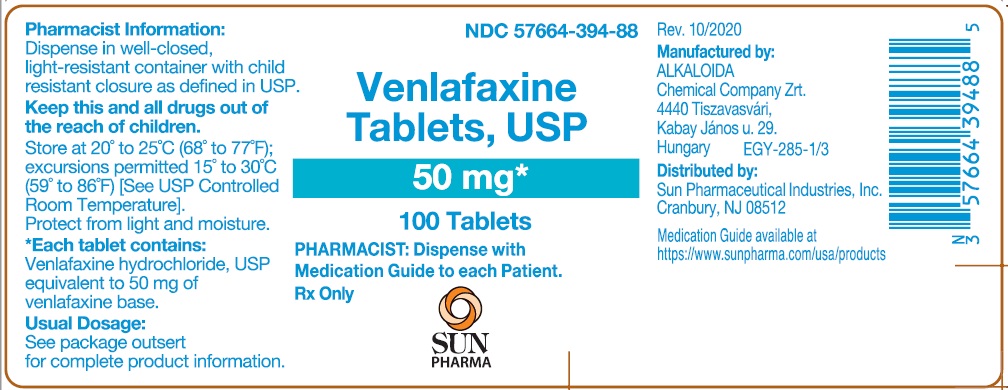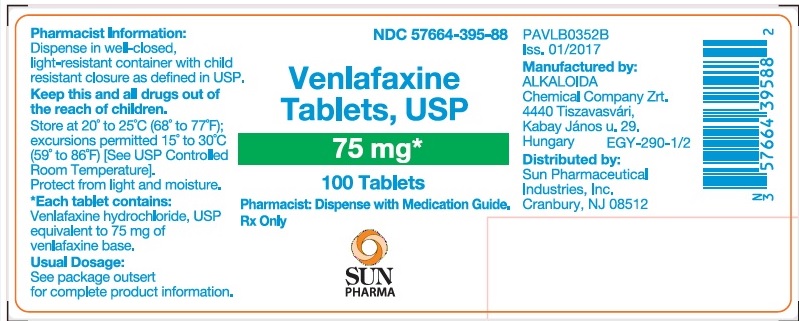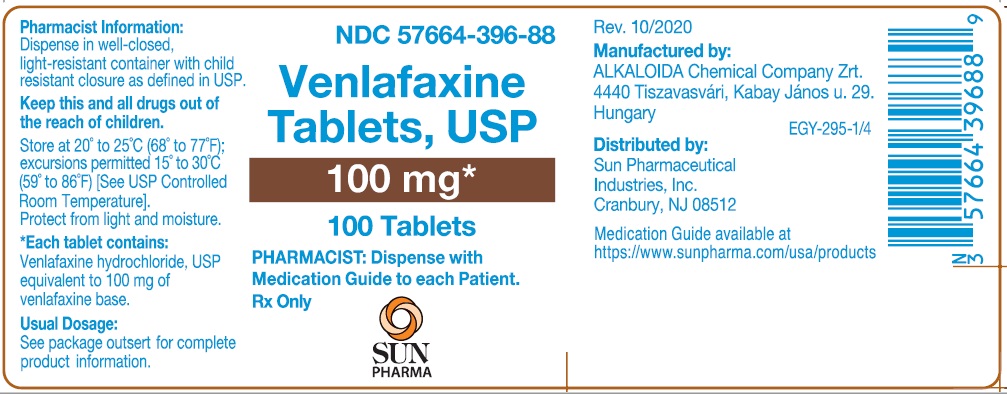 DRUG LABEL: Venlafaxine
NDC: 57664-392 | Form: TABLET
Manufacturer: Sun Pharmaceutical Industries, Inc.
Category: prescription | Type: HUMAN PRESCRIPTION DRUG LABEL
Date: 20260211

ACTIVE INGREDIENTS: VENLAFAXINE HYDROCHLORIDE 25 mg/1 1
INACTIVE INGREDIENTS: MICROCRYSTALLINE CELLULOSE; LACTOSE MONOHYDRATE; STARCH, CORN; SODIUM STARCH GLYCOLATE TYPE A POTATO; FERRIC OXIDE RED; FERRIC OXIDE YELLOW; MAGNESIUM STEARATE; SILICON DIOXIDE

Venlafaxine Tablets, USP

Rx Only

Suicidality and Antidepressant Drugs

Antidepressants increased the risk compared to placebo of suicidal thinking and behavior (suicidality) in children, adolescents, and young adults in short-term studies of Major Depressive Disorder (MDD) and other psychiatric disorders. Anyone considering the use of venlafaxine tablets, USP or any other antidepressant in a child, adolescent, or young adult must balance this risk with the clinical need. Short-term studies did not show an increase in the risk of suicidality with antidepressants compared to placebo in adults beyond age 24; there was a reduction in risk with antidepressants compared to placebo in adults aged 65 and older. Depression and certain other psychiatric disorders are themselves associated with increases in the risk of suicide. Patients of all ages who are started on antidepressant therapy should be monitored appropriately and observed closely for clinical worsening, suicidality, or unusual changes in behavior. Families and caregivers should be advised of the need for close observation and communication with the prescriber. Venlafaxine tablets, USP is not approved for use in pediatric patients. (See WARNINGS: Clinical Worsening and Suicide Risk, PRECAUTIONS: Information for Patients, and PRECAUTIONS: Pediatric Use).

DESCRIPTION

Venlafaxine tablets, USP is a structurally novel antidepressant for oral administration. It is designated (R/S)-1-[2-(dimethylamino)-1-(4-methoxyphenyl)ethyl] cyclohexanol hydrochloride or (±)-1-[α-[(dimethylamino)methyl]-p-methoxybenzyl]cyclohexanol hydrochloride and has the empirical formula of C17H27NO2HCl. Its molecular weight is 313.87. The structural formula is shown below.

Venlafaxine hydrochloride is a white to off-white crystalline solid with a solubility of 572 mg/mL in water (adjusted to ionic strength of 0.2 M with sodium chloride). Its octanol:water (0.2 M sodium chloride) partition coefficient is 0.43.

Compressed tablets contain venlafaxine hydrochloride, USP equivalent to 25 mg, 37.5 mg, 50 mg, 75 mg, or 100 mg of venlafaxine base and the following inactive ingredients: microcrystalline cellulose, lactose monohydrate, pregelatinized starch, sodium starch glycolate, iron oxide red, iron oxide yellow, colloidal silicon dioxide, and magnesium stearate.

CLINICAL PHARMACOLOGY

Pharmacodynamics

The mechanism of the antidepressant action of venlafaxine in humans is believed to be associated with its potentiation of neurotransmitter activity in the CNS. Preclinical studies have shown that venlafaxine and its active metabolite, O-desmethylvenlafaxine (ODV), are potent inhibitors of neuronal serotonin and norepinephrine reuptake and weak inhibitors of dopamine reuptake. Venlafaxine and ODV have no significant affinity for muscarinic, histaminergic, or α-1 adrenergic receptors in vitro. Pharmacologic activity at these receptors is hypothesized to be associated with the various anticholinergic, sedative, and cardiovascular effects seen with other psychotropic drugs. Venlafaxine and ODV do not possess monoamine oxidase (MAO) inhibitory activity.

Pharmacokinetics
Venlafaxine is well absorbed and extensively metabolized in the liver. O-desmethylvenlafaxine (ODV) is the only major active metabolite. On the basis of mass balance studies, at least 92% of a single dose of venlafaxine is absorbed. Approximately 87% of a venlafaxine dose is recovered in the urine within 48 hours as either unchanged venlafaxine (5%), unconjugated ODV (29%), conjugated ODV (26%), or other minor inactive metabolites (27%). Renal elimination of venlafaxine and its metabolites is the primary route of excretion. The relative bioavailability of venlafaxine from a tablet was 100% when compared to an oral solution. Food has no significant effect on the absorption of venlafaxine or on the formation of ODV.

The degree of binding of venlafaxine to human plasma is 27% ± 2% at concentrations ranging from 2.5 to 2215 ng/mL. The degree of ODV binding to human plasma is 30% ± 12% at concentrations ranging from 100 to 500 ng/mL. Protein-binding-induced drug interactions with venlafaxine are not expected.

Steady-state concentrations of both venlafaxine and ODV in plasma were attained within 3 days of multiple-dose therapy. Venlafaxine and ODV exhibited linear kinetics over the dose range of 75 to 450 mg total dose per day (administered on a q8h schedule). Plasma clearance, elimination half-life and steady-state volume of distribution were unaltered for both venlafaxine and ODV after multiple-dosing. Mean ± SD steady-state plasma clearance of venlafaxine and ODV is 1.3　±　0.6 and 0.4 ± 0.2 L/h/kg, respectively; elimination half-life is 5 ± 2 and 11 ± 2 hours, respectively; and steady-state volume of distribution is 7.5 ± 3.7 L/kg and 5.7 ± 1.8 L/kg, respectively. When equal daily doses of venlafaxine were administered as either b.i.d. or t.i.d. regimens, the drug exposure (AUC) and fluctuation in plasma levels of venlafaxine and ODV were comparable following both regimens.

Age and Gender

A pharmacokinetic analysis of 404 venlafaxine-treated patients from two studies involving both b.i.d. and t.i.d. regimens showed that dose-normalized trough plasma levels of either venlafaxine or ODV were unaltered due to age or gender differences. Dosage adjustment based upon the age or gender of a patient is generally not necessary (see DOSAGE AND ADMINISTRATION).

Liver Disease

In 9 subjects with hepatic cirrhosis, the pharmacokinetic disposition of both venlafaxine and ODV was significantly altered after oral administration of venlafaxine. Venlafaxine elimination half-life was prolonged by about 30%, and clearance decreased by about 50% in cirrhotic subjects compared to normal subjects. ODV elimination half-life was prolonged by about 60% and clearance decreased by about 30% in cirrhotic subjects compared to normal subjects. A large degree of intersubject variability was noted. Three patients with more severe cirrhosis had a more substantial decrease in venlafaxine clearance (about 90%) compared to normal subjects.

In a second study, venlafaxine was administered orally and intravenously in normal (n = 21) subjects, and in Child-Pugh A (n = 8) and Child-Pugh B (n = 11) subjects (mildly and moderately impaired, respectively). Venlafaxine oral bioavailability was increased 2 to 3 fold, oral elimination half-life was approximately twice as long and oral clearance was reduced by more than half, compared to normal subjects. In hepatically impaired subjects, ODV oral elimination half-life was prolonged by about 40%, while oral clearance for ODV was similar to that for normal subjects. A large degree of intersubject variability was noted.

Dosage adjustment is necessary in these hepatically impaired patients (see DOSAGE AND ADMINISTRATION).

Renal Disease

In a renal impairment study, venlafaxine elimination half-life after oral administration was prolonged by about 50% and clearance was reduced by about 24% in renally impaired patients (GFR = 10 to 70 mL/min), compared to normal subjects. In dialysis patients, venlafaxine elimination half-life was prolonged by about 180% and clearance was reduced by about 57% compared to normal subjects. Similarly, ODV elimination half-life was prolonged by about 40% although clearance was unchanged in patients with renal impairment (GFR = 10 to 70 mL/min) compared to normal subjects. In dialysis patients, ODV elimination half-life was prolonged by about 142% and clearance was reduced by about 56%, compared to normal subjects. A large degree of intersubject variability was noted.

Dosage adjustment is necessary in these patients (see DOSAGE AND ADMINISTRATION).

CLINICAL TRIALS

The efficacy of venlafaxine tablets, USP as a treatment for major depressive disorder was established in 5 placebo-controlled, short-term trials. Four of these were 6 week trials in adult outpatients meeting DSM-III or DSM-III-R criteria for major depression: two involving dose titration with venlafaxine tablets, USP in a range of 75 to 225 mg/day (t.i.d. schedule), the third involving fixed venlafaxine tablets, USP doses of 75, 225, and 375 mg/day (t.i.d. schedule), and the fourth involving doses of 25, 75, and 200 mg/day (b.i.d. schedule). The fifth was a 4 week study of adult inpatients meeting DSM-III-R criteria for major depression with melancholia whose venlafaxine tablets, USP doses were titrated in a range of 150 to 375 mg/day (t.i.d. schedule). In these 5 studies, venlafaxine tablets, USP was shown to be significantly superior to placebo on at least 2 of the following 3 measures: Hamilton Depression Rating Scale (total score), Hamilton depressed mood item, and Clinical Global Impression-Severity of Illness rating. Doses from 75 to 225 mg/day were superior to placebo in outpatient studies and a mean dose of about 350 mg/day was effective in inpatients. Data from the 2 fixed-dose outpatient studies were suggestive of a dose-response relationship in the range of 75 to 225 mg/day. There was no suggestion of increased response with doses greater than 225 mg/day.

While there were no efficacy studies focusing specifically on an elderly population, elderly patients were included among the patients studied. Overall, approximately 2/3 of all patients in these trials were women. Exploratory analyses for age and gender effects on outcome did not suggest any differential responsiveness on the basis of age or sex.

In one longer-term study, adult outpatients meeting DSM-IV criteria for major depressive disorder who had responded during an 8 week open trial on venlafaxine hydrochloride extended-release capsules (75, 150, or 225 mg, qAM) were randomized to continuation of their same venlafaxine hydrochloride extended-release capsule dose or to placebo, for up to 26 weeks of observation for relapse. Response during the open phase was defined as a CGI Severity of Illness item score of ≤ 3 and a HAM-D-21 total score of ≤ 10 at the day 56 evaluation. Relapse during the double-blind phase was defined as follows: (1) a reappearance of major depressive disorder as defined by DSM-IV criteria and a CGI Severity of Illness item score of ≥ 4 (moderately ill), (2) 2 consecutive CGI Severity of Illness item scores of ≥ 4, or (3) a final CGI Severity of Illness item score of ≥ 4 for any patient who withdrew from the study for any reason. Patients receiving continued venlafaxine hydrochloride extended-release capsule treatment experienced significantly lower relapse rates over the subsequent 26 weeks compared with those receiving placebo.

In a second longer-term trial, adult outpatients meeting DSM-III-R criteria for major depression, recurrent type, who had responded (HAM-D-21 total score ≤ 12 at the day 56 evaluation) and continued to be improved [defined as the following criteria being met for days 56 through 180: (1) no HAM-D-21 total score ≥ 20; (2) no more than 2 HAM-D-21 total scores >10; and (3) no single CGI Severity of Illness item score ≥ 4 (moderately ill)] during an initial 26 weeks of treatment on venlafaxine tablets, USP (100 to 200 mg/day, on a b.i.d. schedule) were randomized to continuation of their same venlafaxine tablets, USP dose or to placebo. The follow-up period to observe patients for relapse, defined as a CGI Severity of Illness item score ≥ 4, was for up to 52 weeks. Patients receiving continued venlafaxine tablets, USP treatment experienced significantly lower relapse rates over the subsequent 52 weeks compared with those receiving placebo.

INDICATIONS AND USAGE

Venlafaxine tablets, USP is indicated for the treatment of major depressive disorder.

The efficacy of venlafaxine tablets, USP in the treatment of major depressive disorder was established in 6 week controlled trials of adult outpatients whose diagnoses corresponded most closely to the DSM-III or DSM-III-R category of major depression and in a 4 week controlled trial of inpatients meeting diagnostic criteria for major depression with melancholia (see CLINICAL TRIALS).

A major depressive episode implies a prominent and relatively persistent depressed or dysphoric mood that usually interferes with daily functioning (nearly every day for at least 2 weeks); it should include at least 4 of the following 8 symptoms: change in appetite, change in sleep, psychomotor agitation or retardation, loss of interest in usual activities or decrease in sexual drive, increased fatigue, feelings of guilt or worthlessness, slowed thinking or impaired concentration, and a suicide attempt or suicidal ideation.

The efficacy of venlafaxine hydrochloride extended-release capsules in maintaining an antidepressant response for up to 26 weeks following 8 weeks of acute treatment was demonstrated in a placebo-controlled trial. The efficacy of venlafaxine tablets, USP in maintaining an antidepressant response in patients with recurrent depression who had responded and continued to be improved during an initial 26 weeks of treatment and were then followed for a period of up to 52 weeks was demonstrated in a second placebo-controlled trial (see CLINICAL TRIALS). Nevertheless, the physician who elects to use venlafaxine tablets, USP/venlafaxine hydrochloride extended-release capsules for extended periods should periodically re-evaluate the long-term usefulness of the drug for the individual patient.

CONTRAINDICATIONS

Hypersensitivity to venlafaxine hydrochloride or to any excipients in the formulation.

The use of MAOIs intended to treat psychiatric disorders with Venlafaxine tablets, USP or within 7 days of stopping treatment with venlafaxine tablets, USP is contraindicated because of an increased risk of serotonin syndrome. The use of Venlafaxine tablets, USP within 14 days of stopping an MAOI intended to treat psychiatric disorders is also contraindicated (see WARNINGSand DOSAGE AND ADMINISTRATION).

Starting venlafaxine tablets, USP in a patient who is being treated with MAOIs such as linezolid or intravenous methylene blue is also contraindicated because of an increased risk of serotonin syndrome (see WARNINGSand DOSAGE AND ADMINISTRATION).

WARNINGS

Clinical Worsening and Suicide Risk

Patients with major depressive disorder (MDD), both adult and pediatric, may experience worsening of their depression and/or the emergence of suicidal ideation and behavior (suicidality) or unusual changes in behavior, whether or not they are taking antidepressant medications, and this risk may persist until significant remission occurs. Suicide is a known risk of depression and certain other psychiatric disorders, and these disorders themselves are the strongest predictors of suicide. There has been a long standing concern, however, that antidepressants may have a role in inducing worsening of depression and the emergence of suicidality in certain patients during the early phases of treatment. Pooled analyses of short-term placebo-controlled trials of antidepressant drugs (SSRIs and others) showed that these drugs increase the risk of suicidal thinking and behavior (suicidality) in children, adolescents, and young adults (ages 18 to 24) with major depressive disorder (MDD) and other psychiatric disorders. Short-term studies did not show an increase in the risk of suicidality with antidepressants compared to placebo in adults beyond age 24; there was a reduction with antidepressants compared to placebo in adults aged 65 and older.

The pooled analyses of placebo-controlled trials in children and adolescents with MDD, obsessive compulsive disorder (OCD), or other psychiatric disorders included a total of 24 short-term trials of 9 antidepressant drugs in over 4400 patients. The pooled analyses of placebo-controlled trials in adults with MDD or other psychiatric disorders included a total of 295 short-term trials (median duration of 2 months) of 11 antidepressant drugs in over 77,000 patients. There was considerable variation in risk of suicidality among drugs, but a tendency toward an increase in the younger patients for almost all drugs studied. There were differences in absolute risk of suicidality across the different indications, with the highest incidence in MDD. The risk differences (drug vs placebo), however, were relatively stable within age strata and across indications. These risk differences (drug-placebo difference in the number of cases of suicidality per 1000 patients treated) are provided in Table 1.

Table 1:
Age Range | Drug-Placebo Difference in Number of Cases of Suicidality per 1000 Patients Treated
 | Increases Compared to Placebo
<18 | 14 additional cases
18 to 24 | 5 additional cases
 | Decreases Compared to Placebo
25 to 64 | 1 fewer case
≥65 | 6 fewer cases

No suicides occurred in any of the pediatric trials. There were suicides in the adult trials, but the number was not sufficient to reach any conclusion about drug effect on suicide.

It is unknown whether the suicidality risk extends to longer-term use, i.e., beyond several months. However, there is substantial evidence from placebo-controlled maintenance trials in adults with depression that the use of antidepressants can delay the recurrence of depression.

All patients being treated with antidepressants for any indication should be monitored appropriately and observed closely for clinical worsening, suicidality, and unusual changes in behavior, especially during the initial few months of a course of drug therapy, or at times of dose changes, either increases or decreases.

The following symptoms, anxiety, agitation, panic attacks, insomnia, irritability, hostility, aggressiveness, impulsivity, akathisia (psychomotor restlessness), hypomania, and mania, have been reported in adult and pediatric patients being treated with antidepressants for major depressive disorder as well as for other indications, both psychiatric and nonpsychiatric. Although a causal link between the emergence of such symptoms and either the worsening of depression and/or the emergence of suicidal impulses has not been established, there is concern that such symptoms may represent precursors to emerging suicidality.

Consideration should be given to changing the therapeutic regimen, including possibly discontinuing the medication, in patients whose depression is persistently worse, or who are experiencing emergent suicidality or symptoms that might be precursors to worsening depression or suicidality, especially if these symptoms are severe, abrupt in onset, or were not part of the patient's presenting symptoms.

If the decision has been made to discontinue treatment, medication should be tapered, as rapidly as is feasible, but with recognition that abrupt discontinuation can be associated with certain symptoms (see PRECAUTIONSand DOSAGE AND ADMINISTRATION, Discontinuing Venlafaxine Tablets, USP, for a description of the risks of discontinuation of venlafaxine tablets, USP).

Families and caregivers of patients being treated with antidepressants for major depressive disorder or other indications, both psychiatric and nonpsychiatric, should be alerted about the need to monitor patients for the emergence of agitation, irritability, unusual changes in behavior, and the other symptoms described above, as well as the emergence of suicidality, and to report such symptoms immediately to healthcare providers. Such monitoring should include daily observation by families and caregivers.Prescriptions for venlafaxine tablets, USP should be written for the smallest quantity of tablets consistent with good patient management, in order to reduce the risk of overdose.

Screening Patients for Bipolar Disorder

A major depressive episode may be the initial presentation of bipolar disorder. It is generally believed (though not established in controlled trials) that treating such an episode with an antidepressant alone may increase the likelihood of precipitation of a mixed/manic episode in patients at risk for bipolar disorder. Whether any of the symptoms described above represent such a conversion is unknown. However, prior to initiating treatment with an antidepressant, patients with depressive symptoms should be adequately screened to determine if they are at risk for bipolar disorder; such screening should include a detailed psychiatric history, including a family history of suicide, bipolar disorder, and depression. It should be noted that venlafaxine tablets, USP are not approved for use in treating bipolar depression.

Serotonin Syndrome

The development of a potentially life-threatening serotonin syndrome has been reported with SNRIs and SSRIs, including venlafaxine tablets, USP, alone but particularly with concomitant use of other serotonergic drugs (including triptans, tricyclic antidepressants, fentanyl, lithium, tramadol, meperidine, methadone, tryptophan, buspirone, amphetamines, and St. John's Wort) and with drugs that impair metabolism of serotonin (in particular, MAOIs, both those intended to treat psychiatric disorders and also others, such as linezolid and intravenous methylene blue).

Serotonin syndrome symptoms may include mental status changes (e.g., agitation, hallucinations, delirium, and coma), autonomic instability (e.g., tachycardia, labile blood pressure, dizziness, diaphoresis, flushing, hyperthermia), neuromuscular symptoms (e.g., tremor, rigidity, myoclonus, hyperreflexia, incoordination), seizures, and/or gastrointestinal symptoms (e.g., nausea, vomiting, diarrhea). Patients should be monitored for the emergence of serotonin syndrome.

The concomitant use of venlafaxine tablets, USP with MAOIs intended to treat psychiatric disorders is contraindicated. Venlafaxine tablets, USP should also not be started in a patient who is being treated with MAOIs such as linezolid or intravenous methylene blue. All reports with methylene blue that provided information on the route of administration involved intravenous administration in the dose range of 1 mg/kg to 8 mg/kg. No reports involved the administration of methylene blue by other routes (such as oral tablets or local tissue injection) or at lower doses. There may be circumstances when it is necessary to initiate treatment with a MAOI such as linezolid or intravenous methylene blue in a patient taking venlafaxine tablets, USP. Venlafaxine tablets, USP should be discontinued before initiating treatment with the MAOI (see CONTRAINDICATIONSand DOSAGE AND ADMINISTRATION).

If concomitant use of venlafaxine tablets, USP with other serotonergic drugs, including triptans, tricyclic antidepressants, fentanyl, lithium, tramadol, buspirone, tryptophan, amphetamines, and St. John's Wort is clinically warranted, patients should be made aware of a potential increased risk of serotonin syndrome, particularly during treatment initiation and dose increases.

Treatment with venlafaxine tablets, USP and any concomitant serotonergic agents should be discontinued immediately if the above events occur and supportive symptomatic treatment should be initiated.

Angle-Closure Glaucoma

The pupillary dilation that occurs following use of many antidepressant drugs including venlafaxine tablets, USP may trigger an angle closure attack in a patient with anatomically narrow angles who does not have a patent iridectomy.

Sustained Hypertension

Venlafaxine treatment is associated with sustained increases in blood pressure in some patients. (1) In a premarketing study comparing three fixed doses of venlafaxine (75, 225, and 375 mg/day) and placebo, a mean increase in supine diastolic blood pressure (SDBP) of 7.2 mm Hg was seen in the 375 mg/day group at week 6 compared to essentially no changes in the 75 and 225 mg/day groups and a mean decrease in SDBP of 2.2 mm Hg in the placebo group. (2) An analysis for patients meeting criteria for sustained hypertension (defined as treatment-emergent SDBP ≥ 90 mm Hg and ≥ 10 mm Hg above baseline for 3 consecutive visits) revealed a dose-dependent increase in the incidence of sustained hypertension for venlafaxine:

Probability of Sustained Elevation in SDBP (Pool of Premarketing Venlafaxine Studies)
Treatment Group | Incidence of Sustained Elevation in SDBP
Venlafaxine
< 100 mg/day | 3%
101 to 200 mg/day | 5%
201 to 300 mg/day | 7%
> 300 mg/day | 13%
Placebo | 2%

An analysis of the patients with sustained hypertension and the 19 venlafaxine patients who were discontinued from treatment because of hypertension (<1% of total venlafaxine-treated group) revealed that most of the blood pressure increases were in a modest range (10 to 15 mm Hg, SDBP). Nevertheless, sustained increases of this magnitude could have adverse consequences. Cases of elevated blood pressure requiring immediate treatment have been reported in postmarketing experience. Preexisting hypertension should be controlled before treatment with venlafaxine. It is recommended that patients receiving venlafaxine have regular monitoring of blood pressure. For patients who experience a sustained increase in blood pressure while receiving venlafaxine, either dose reduction or discontinuation should be considered.

Mydriasis

Mydriasis has been reported in association with venlafaxine; therefore patients at risk of acute narrow-angle glaucoma (angle-closure glaucoma) should be monitored (see PRECAUTIONS, Information for Patients).

Sexual Dysfunction

Use of SNRIs, including venlafaxine tablets, USP, may cause symptoms of sexual dysfunction (see ADVERSE REACTIONS). In male patients, SNRI use may result in ejaculatory delay or failure, decreased libido, and erectile dysfunction. In female patients, SNRI use may result in decreased libido and delayed or absent orgasm.

It is important for prescribers to inquire about sexual function prior to initiation of venlafaxine tablets, USP and to inquire specifically about changes in sexual function during treatment, because sexual function may not be spontaneously reported. When evaluating changes in sexual function, obtaining a detailed history (including timing of symptom onset) is important because sexual symptoms may have other causes, including the underlying psychiatric disorder. Discuss potential management strategies to support patients in making informed decisions about treatment.

PRECAUTIONS

General

Discontinuation of Treatment with Venlafaxine Tablets, USP

Discontinuation symptoms have been systematically evaluated in patients taking venlafaxine, to include prospective analyses of clinical trials in Generalized Anxiety Disorder and retrospective surveys of trials in major depressive disorder. Abrupt discontinuation or dose reduction of venlafaxine at various doses has been found to be associated with the appearance of new symptoms, the frequency of which increased with increased dose level and with longer duration of treatment. Reported symptoms include agitation, anorexia, anxiety, confusion, impaired coordination and balance, diarrhea, dizziness, dry mouth, dysphoric mood, fasciculation, fatigue, flu-like symptoms, headaches, hypomania, insomnia, nausea, nervousness, nightmares, sensory disturbances (including shock-like electrical sensations), somnolence, sweating, tremor, vertigo, and vomiting.

During marketing of venlafaxine tablets, USP, other SNRIs (Serotonin and Norepinephrine Reuptake Inhibitors), and SSRIs (Selective Serotonin Reuptake Inhibitors), there have been spontaneous reports of adverse events occurring upon discontinuation of these drugs, particularly when abrupt, including the following: dysphoric mood, irritability, agitation, dizziness, sensory disturbances (e.g. paresthesias such as electric shock sensations), anxiety, confusion, headache, lethargy, emotional lability, insomnia, hypomania, tinnitus, and seizures. While these events are generally self-limiting, there have been reports of serious discontinuation symptoms.

Patients should be monitored for these symptoms when discontinuing treatment with venlafaxine tablets, USP. A gradual reduction in the dose rather than abrupt cessation is recommended whenever possible. If intolerable symptoms occur following a decrease in the dose or upon discontinuation of treatment, then resuming the previously prescribed dose may be considered. Subsequently, the physician may continue decreasing the dose but at a more gradual rate (see DOSAGE AND ADMINISTRATION).

Anxiety and Insomnia
Treatment-emergent anxiety, nervousness, and insomnia were more commonly reported for venlafaxine-treated patients compared to placebo-treated patients in a pooled analysis of short-term, double-blind, placebo-controlled depression studies:

 | Venlafaxine | Placebo
Symptom | n = 1033 | n = 609
Anxiety | 6% | 3%
Nervousness | 13% | 6%
Insomnia | 18% | 10%

Anxiety, nervousness, and insomnia led to drug discontinuation in 2%, 2%, and 3%, respectively, of the patients treated with venlafaxine in the Phase 2 and Phase 3 depression studies.

Changes in Weight

Adult Patients

A dose-dependent weight loss was noted in patients treated with venlafaxine for several weeks. A loss of 5% or more of body weight occurred in 6% of patients treated with venlafaxine compared with 1% of patients treated with placebo and 3% of patients treated with another antidepressant. However, discontinuation for weight loss associated with venlafaxine was uncommon (0.1% of venlafaxine-treated patients in the Phase 2 and Phase 3 depression trials).

The safety and efficacy of venlafaxine therapy in combination with weight loss agents, including phentermine, have not been established. Coadministration of venlafaxine tablets, USP and weight loss agents is not recommended. Venlafaxine tablets, USP is not indicated for weight loss alone or in combination with other products.

Pediatric Patients

Weight loss has been observed in pediatric patients (ages 6 to 17) receiving venlafaxine hydrochloride extended-release capsules. In a pooled analysis of four eight-week, double-blind, placebo-controlled, flexible dose outpatient trials for major depressive disorder (MDD) and generalized anxiety disorder (GAD), venlafaxine hydrochloride extended-release capsule-treated patients lost an average of 0.45 kg (n = 333), while placebo-treated patients gained an average of 0.77 kg (n = 333). More patients treated with venlafaxine hydrochloride extended-release capsules than with placebo experienced a weight loss of at least 3.5% in both the MDD and the GAD studies (18% of venlafaxine hydrochloride extended-release capsule-treated patients vs. 3.6% of placebo-treated patients; p<0.001). Weight loss was not limited to patients with treatment-emergent anorexia (see PRECAUTIONS, General, Changes in Appetite).

The risks associated with longer-term venlafaxine hydrochloride extended-release capsule use were assessed in an open-label study of children and adolescents who received venlafaxine hydrochloride extended-release capsules for up to six months. The children and adolescents in the study had increases in weight that were less than expected based on data from age- and sex-matched peers. The difference between observed weight gain and expected weight gain was larger for children (<12 years old) than for adolescents (>12 years old).

Changes in Height

Pediatric Patients

During the eight-week placebo-controlled GAD studies, venlafaxine hydrochloride extended-release capsule-treated patients (ages 6 to 17) grew an average of 0.3 cm (n = 122), while placebo-treated patients grew an average of 1.0 cm (n = 132); p = 0.041. This difference in height increase was most notable in patients younger than twelve. During the eight-week placebo-controlled MDD studies, venlafaxine hydrochloride extended-release capsule-treated patients grew an average of 0.8 cm (n = 146), while placebo-treated patients grew an average of 0.7 cm (n = 147). In the six-month open-label study, children and adolescents had height increases that were less than expected based on data from age- and sex-matched peers. The difference between observed growth rates and expected growth rates was larger for children (<12 years old) than for adolescents (>12 years old).

Changes in Appetite

Adult Patients

Treatment-emergent anorexia was more commonly reported for venlafaxine-treated (11%) than placebo-treated patients (2%) in the pool of short-term, double-blind, placebo-controlled depression studies.

Pediatric Patients

Decreased appetite has been observed in pediatric patients receiving venlafaxine hydrochloride extended-release capsules. In the placebo-controlled trials for GAD and MDD, 10% of patients aged 6 to 17 treated with venlafaxine hydrochloride extended-release capsules for up to eight weeks and 3% of patients treated with placebo reported treatment-emergent anorexia (decreased appetite). None of the patients receiving venlafaxine hydrochloride extended-release capsules discontinued for anorexia or weight loss.

Activation of Mania/Hypomania

During Phase 2 and Phase 3 trials, hypomania or mania occurred in 0.5% of patients treated with venlafaxine. Activation of mania/hypomania has also been reported in a small proportion of patients with major affective disorder who were treated with other marketed antidepressants. As with all antidepressants, venlafaxine tablets, USP should be used cautiously in patients with a history of mania.

Hyponatremia

Hyponatremia may occur as a result of treatment with SSRIs and SNRIs, including venlafaxine tablets, USP. In many cases, this hyponatremia appears to be the result of the syndrome of inappropriate antidiuretic hormone secretion (SIADH). Cases with serum sodium lower than 110 mmol/L have been reported. Elderly patients may be at greater risk of developing hyponatremia with SSRIs and SNRIs. Also, patients taking diuretics or who are otherwise volume depleted may be at greater risk (see PRECAUTIONS, Geriatric Use). Discontinuation of venlafaxine tablets, USP should be considered in patients with symptomatic hyponatremia and appropriate medical intervention should be instituted.

Signs and symptoms of hyponatremia include headache, difficulty concentrating, memory impairment, confusion, weakness, and unsteadiness, which may lead to falls. Signs and symptoms associated with more severe and/or acute cases have included hallucination, syncope, seizure, coma, respiratory arrest, and death.

Seizures

During premarketing testing, seizures were reported in 0.26% (8/3082) of venlafaxine-treated patients. Most seizures (5 of 8) occurred in patients receiving doses of 150 mg/day or less. Venlafaxine tablets, USP should be used cautiously in patients with a history of seizures. It should be discontinued in any patient who develops seizures.

Abnormal Bleeding

SSRIs and SNRIs, including venlafaxine tablets, USP, may increase the risk of bleeding events. Concomitant use of aspirin, non-steroidal anti-inflammatory drugs, warfarin, and other anti-coagulants may add to this risk. Case reports and epidemiological studies (case-control and cohort design) have demonstrated an association between use of drugs that interfere with serotonin reuptake and the occurrence of gastrointestinal bleeding. Based on data from the published observational studies, exposure to SSRIs, particularly in the month before delivery, has been associated with a less than 2-fold increase in the risk of postpartum hemorrhage (see Pregnancy). Bleeding events related to SSRIs and SNRIs use have ranged from ecchymoses, hematomas, epistaxis, and petechiae to life-threatening hemorrhages.

Patients should be cautioned about the increased risk of bleeding associated with the concomitant use of venlafaxine tablets, USP and NSAIDs, aspirin, or other drugs that affect coagulation.

Serum Cholesterol Elevation

Clinically relevant increases in serum cholesterol were recorded in 5.3% of venlafaxine-treated patients and 0.0% of placebo-treated patients treated for at least 3 months in placebo-controlled trials (see ADVERSE REACTIONS, Laboratory Changes). Measurement of serum cholesterol levels should be considered during long-term treatment.

Interstitial Lung Disease and Eosinophilic Pneumonia
Interstitial lung disease and eosinophilic pneumonia associated with venlafaxine therapy have been rarely reported. The possibility of these adverse events should be considered in venlafaxine-treated patients who present with progressive dyspnea, cough or chest discomfort. Such patients should undergo a prompt medical evaluation and discontinuation of venlafaxine therapy should be considered.

Use in Patients With Concomitant Illness

Clinical experience with venlafaxine tablets, USP in patients with concomitant systemic illness is limited. Caution is advised in administering venlafaxine tablets, USP to patients with diseases or conditions that could affect hemodynamic responses or metabolism.

Venlafaxine tablets, USP has not been evaluated or used to any appreciable extent in patients with a recent history of myocardial infarction or unstable heart disease. Patients with these diagnoses were systematically excluded from many clinical studies during the product's premarketing testing. Evaluation of the electrocardiograms for 769 patients who received venlafaxine tablets, USP in 4 to 6 week double-blind placebo-controlled trials, however, showed that the incidence of trial-emergent conduction abnormalities did not differ from that with placebo. The mean heart rate in venlafaxine tablets, USP-treated patients was increased relative to baseline by about 4 beats per minute.

The electrocardiograms for 357 patients who received venlafaxine hydrochloride extended-release capsules and 285 patients who received placebo in 8 to 12 week double-blind, placebo-controlled trials were analyzed. The mean change from baseline in corrected QT interval (QTc) for venlafaxine hydrochloride extended-release capsule-treated patients was increased relative to that for placebo-treated patients (increase of 4.7 msec for venlafaxine hydrochloride extended-release capsules and decrease of 1.9 msec for placebo). In these same trials, the mean change from baseline in heart rate for venlafaxine hydrochloride extended-release capsule-treated patients was significantly higher than that for placebo (a mean increase of 4 beats per minute for venlafaxine hydrochloride extended-release capsules and 1 beat per minute for placebo). In a flexible-dose study, with venlafaxine tablets, USP doses in the range of 200 to 375 mg/day and mean dose greater than 300 mg/day, venlafaxine tablets, USP-treated patients had a mean increase in heart rate of 8.5 beats per minute compared with 1.7 beats per minute in the placebo group.

As increases in heart rate were observed, caution should be exercised in patients whose underlying medical conditions might be compromised by increases in heart rate (e.g., patients with hyperthyroidism, heart failure, or recent myocardial infarction), particularly when using doses of venlafaxine tablets, USP above 200 mg/day.

In patients with renal impairment (GFR=10 to 70 mL/min) or cirrhosis of the liver, the clearances of venlafaxine and its active metabolite were decreased, thus prolonging the elimination half-lives of these substances. A lower dose may be necessary (see DOSAGE AND ADMINISTRATION). Venlafaxine tablets, USP, like all antidepressants, should be used with caution in such patients.

Information for Patients

Prescribers or other health professionals should inform patients, their families, and their caregivers about the benefits and risks associated with treatment with venlafaxine tablets, USP and should counsel them in its appropriate use. A patient Medication Guide about "Antidepressant Medicines, Depression and other Serious Mental Illness, and Suicidal Thoughts or Actions" is available for venlafaxine tablets, USP. The prescriber or health professional should instruct patients, their families, and their caregivers to read the Medication Guide and should assist them in understanding its contents. Patients should be given the opportunity to discuss the contents of the Medication Guide and to obtain answers to any questions they may have. The complete text of the Medication Guide is reprinted at the end of this document.

Patients should be advised of the following issues and asked to alert their prescriber if these occur while taking venlafaxine tablets, USP.

Clinical Worsening and Suicide Risk

Patients, their families, and their caregivers should be encouraged to be alert to the emergence of anxiety, agitation, panic attacks, insomnia, irritability, hostility, aggressiveness, impulsivity, akathisia (psychomotor restlessness), hypomania, mania, other unusual changes in behavior, worsening of depression, and suicidal ideation, especially early during antidepressant treatment and when the dose is adjusted up or down. Families and caregivers of patients should be advised to look for the emergence of such symptoms on a day-to-day basis, since changes may be abrupt. Such symptoms should be reported to the patient's prescriber or health professional, especially if they are severe, abrupt in onset, or were not part of the patient's presenting symptoms. Symptoms such as these may be associated with an increased risk for suicidal thinking and behavior and indicate a need for very close monitoring and possibly changes in the medication.

Interference with Cognitive and Motor Performance

Clinical studies were performed to examine the effects of venlafaxine on behavioral performance of healthy individuals. The results revealed no clinically significant impairment of psychomotor, cognitive, or complex behavior performance. However, since any psychoactive drug may impair judgment, thinking, or motor skills, patients should be cautioned about operating hazardous machinery, including automobiles, until they are reasonably certain that venlafaxine tablets, USP therapy does not adversely affect their ability to engage in such activities.

Angle-Closure Glaucoma

Patients should be advised that taking venlafaxine tablets, USP can cause mild pupillary dilation, which in susceptible individuals, can lead to an episode of angle-closure glaucoma. Preexisting glaucoma is almost always open-angle glaucoma because angle-closure glaucoma, when diagnosed, can be treated definitively with iridectomy. Open-angle glaucoma is not a risk factor for angle-closure glaucoma. Patients may wish to be examined to determine whether they are susceptible to angle closure, and have a prophylactic procedure (e.g., iridectomy), if they are susceptible.

Pregnancy

Patients should be advised to notify their physician if they become pregnant or intend to become pregnant during therapy.

Nursing

Patients should be advised to notify their physician if they are breastfeeding an infant.

Mydriasis

Mydriasis (prolonged dilation of the pupils of the eye) has been reported with venlafaxine. Patients should be advised to notify their physician if they have a history of angle-closure glaucoma or a history of increased intraocular pressure (see WARNINGS).

Sexual Dysfunction

Advise patients that use of venlafaxine tablets, USP may cause symptoms of sexual dysfunction in both male and female patients. Inform patients that they should discuss any changes in sexual function and potential management strategies with their healthcare provider (see WARNINGS).

Concomitant Medication

Patients should be advised to inform their physicians if they are taking, or plan to take, any prescription or over-the-counter drugs, including herbal preparations and nutritional supplements, since there is a potential for interactions.

Patients should be cautioned about the risk of serotonin syndrome with the concomitant use of venlafaxine tablets, USP and triptans, opioids, tryptophan supplements or other serotonergic agents (see CONTRAINDICATIONSand WARNINGS, Serotonin Syndromeand PRECAUTIONS, Drug Interactions, CNS-Active Drugs, Serotonergic Drugs).

Patients should be cautioned about the concomitant use of venlafaxine tablets, USP and NSAIDs, aspirin, warfarin, or other drugs that affect coagulation since combined use of psychotropic drugs that interfere with serotonin reuptake and these agents has been associated with an increased risk of bleeding (see PRECAUTIONS, Abnormal Bleeding).

Alcohol

Although venlafaxine tablets, USP has not been shown to increase the impairment of mental and motor skills caused by alcohol, patients should be advised to avoid alcohol while taking venlafaxine tablets, USP.

Allergic Reactions

Patients should be advised to notify their physician if they develop a rash, hives, or a related allergic phenomenon.

Laboratory Tests

There are no specific laboratory tests recommended.

Drug Interactions

As with all drugs, the potential for interaction by a variety of mechanisms is a possibility.

Alcohol

A single dose of ethanol (0.5 g/kg) had no effect on the pharmacokinetics of venlafaxine or ODV when venlafaxine was administered at 150 mg/day in 15 healthy male subjects. Additionally, administration of venlafaxine in a stable regimen did not exaggerate the psychomotor and psychometric effects induced by ethanol in these same subjects when they were not receiving venlafaxine.

Cimetidine

Concomitant administration of cimetidine and venlafaxine in a steady-state study for both drugs resulted in inhibition of first-pass metabolism of venlafaxine in 18 healthy subjects. The oral clearance of venlafaxine was reduced by about 43%, and the exposure (AUC) and maximum concentration (Cmax) of the drug were increased by about 60%. However, coadministration of cimetidine had no apparent effect on the pharmacokinetics of ODV, which is present in much greater quantity in the circulation than is venlafaxine. The overall pharmacological activity of venlafaxine plus ODV is expected to increase only slightly, and no dosage adjustment should be necessary for most normal adults. However, for patients with preexisting hypertension, and for elderly patients or patients with hepatic dysfunction, the interaction associated with the concomitant use of venlafaxine and cimetidine is not known and potentially could be more pronounced. Therefore, caution is advised with such patients.

Diazepam

Under steady-state conditions for venlafaxine administered at 150 mg/day, a single 10 mg dose of diazepam did not appear to affect the pharmacokinetics of either venlafaxine or ODV in 18 healthy male subjects. Venlafaxine also did not have any effect on the pharmacokinetics of diazepam or its active metabolite, desmethyldiazepam, or affect the psychomotor and psychometric effects induced by diazepam.

Haloperidol

Venlafaxine administered under steady-state conditions at 150 mg/day in 24 healthy subjects decreased total oral-dose clearance (CI/F) of a single 2 mg dose of haloperidol by 42%, which resulted in a 70% increase in haloperidol AUC. In addition, the haloperidol Cmaxincreased 88% when coadministered with venlafaxine, but the haloperidol elimination half-life (t1/2) was unchanged. The mechanism explaining this finding is unknown.

Lithium

The steady-state pharmacokinetics of venlafaxine administered at 150 mg/day were not affected when a single 600 mg oral dose of lithium was administered to 12 healthy male subjects. O-desmethylvenlafaxine (ODV) also was unaffected. Venlafaxine had no effect on the pharmacokinetics of lithium (see also CNS-Active Drugs, below).

Drugs Highly Bound to Plasma Protein

Venlafaxine is not highly bound to plasma proteins; therefore, administration of venlafaxine tablets, USP to a patient taking another drug that is highly protein bound should not cause increased free concentrations of the other drug.

Drugs That Interfere With Hemostasis (e.g., NSAIDs, Aspirin, and Warfarin)

Serotonin release by platelets plays an important role in hemostasis. Epidemiological studies of the case-control and cohort design that have demonstrated an association between use of psychotropic drugs that interfere with serotonin reuptake and the occurrence of upper gastrointestinal bleeding have also shown that concurrent use of an NSAID or aspirin may potentiate this risk of bleeding. Altered anticoagulant effects, including increased bleeding, have been reported when SSRIs and SNRIs are coadministered with warfarin. Patients receiving warfarin therapy should be carefully monitored when venlafaxine tablets, USP is initiated or discontinued.

Drugs That Inhibit Cytochrome P450 Isoenzymes

CYP2D6 Inhibitors

In vitro and in vivo studies indicate that venlafaxine is metabolized to its active metabolite, ODV, by CYP2D6, the isoenzyme that is responsible for the genetic polymorphism seen in the metabolism of many antidepressants. Therefore, the potential exists for a drug interaction between drugs that inhibit CYP2D6-mediated metabolism and venlafaxine. However, although imipramine partially inhibited the CYP2D6-mediated metabolism of venlafaxine, resulting in higher plasma concentrations of venlafaxine and lower plasma concentrations of ODV, the total concentration of active compounds (venlafaxine plus ODV) was not affected. Additionally, in a clinical study involving CYP2D6-poor and -extensive metabolizers, the total concentration of active compounds (venlafaxine plus ODV), was similar in the two metabolizer groups. Therefore, no dosage adjustment is required when venlafaxine is coadministered with a CYP2D6 inhibitor.

Ketoconazole

A pharmacokinetic study with ketoconazole 100 mg b.i.d. with a single dose of venlafaxine 50 mg in extensive metabolizers (EM; n = 14) and 25 mg in poor metabolizers (PM; n = 6) of CYP2D6 resulted in higher plasma concentrations of both venlafaxine and O-desvenlafaxine (ODV) in most subjects following administration of ketoconazole. Venlafaxine Cmaxincreased by 26% in EM subjects and 48% in PM subjects. Cmaxvalues for ODV increased by 14% and 29% in EM and PM subjects, respectively.

Venlafaxine AUC increased by 21% in EM subjects and 70% in PM subjects (range in PMs - 2% to 206%), and AUC values for ODV increased by 23% and 33% in EM and PM subjects (range in PMs - 38% to 105%) subjects, respectively. Combined AUCs of venlafaxine and ODV increased on average by approximately 23% in EMs and 53% in PMs, (range in PMs 4% to 134%).

Concomitant use of CYP3A4 inhibitors and venlafaxine may increase levels of venlafaxine and ODV. Therefore, caution is advised if a patient’s therapy includes a CYP3A4 inhibitor and venlafaxine concomitantly.

CYP3A4 Inhibitors

In vitro studies indicate that venlafaxine is likely metabolized to a minor, less active metabolite, N-desmethylvenlafaxine, by CYP3A4. Because CYP3A4 is typically a minor pathway relative to CYP2D6 in the metabolism of venlafaxine, the potential for a clinically significant drug interaction between drugs that inhibit CYP3A4-mediated metabolism and venlafaxine is small.

The concomitant use of venlafaxine with a drug treatment(s) that potently inhibits both CYP2D6 and CYP3A4, the primary metabolizing enzymes for venlafaxine, has not been studied. Therefore, caution is advised should a patient's therapy include venlafaxine and any agent(s) that produce potent simultaneous inhibition of these two enzyme systems.

Drugs Metabolized by Cytochrome P450 Isoenzymes

CYP2D6

In vitro studies indicate that venlafaxine is a relatively weak inhibitor of CYP2D6. These findings have been confirmed in a clinical drug interaction study comparing the effect of venlafaxine to that of fluoxetine on the CYP2D6-mediated metabolism of dextromethorphan to dextrorphan.

Imipramine

Venlafaxine did not affect the pharmacokinetics of imipramine and 2-OH-imipramine. However, desipramine AUC, Cmax, and Cminincreased by about 35% in the presence of venlafaxine. The 2-OH-desipramine AUCs increased by at least 2.5 fold (with venlafaxine 37.5 mg q12h) and by 4.5 fold (with venlafaxine 75 mg q12h). Imipramine did not affect the pharmacokinetics of venlafaxine and ODV. The clinical significance of elevated 2-OH-desipramine levels is unknown.

Metoprolol

Concomitant administration of venlafaxine (50 mg every 8 hours for 5 days) and metoprolol (100 mg every 24 hours for 5 days) to 18 healthy male subjects in a pharmacokinetic interaction study for both drugs resulted in an increase of plasma concentrations of metoprolol by approximately 30 to 40% without altering the plasma concentrations of its active metabolite, α-hydroxymetoprolol. Metoprolol did not alter the pharmacokinetic profile of venlafaxine or its active metabolite, O-desmethylvenlafaxine.

Venlafaxine appeared to reduce the blood pressure lowering effect of metoprolol in this study. The clinical relevance of this finding for hypertensive patients is unknown. Caution should be exercised with coadministration of venlafaxine and metoprolol.

Venlafaxine treatment has been associated with dose-related increases in blood pressure in some patients. It is recommended that patients receiving venlafaxine tablets, USP have regular monitoring of blood pressure (see WARNINGS).

Risperidone

Venlafaxine administered under steady-state conditions at 150 mg/day slightly inhibited the CYP2D6-mediated metabolism of risperidone (administered as a single 1 mg oral dose) to its active metabolite, 9-hydroxyrisperidone, resulting in an approximate 32% increase in risperidone AUC. However, venlafaxine coadministration did not significantly alter the pharmacokinetic profile of the total active moiety (risperidone plus 9-hydroxyrisperidone).

CYP3A4

Venlafaxine did not inhibit CYP3A4 in vitro. This finding was confirmed in vivo by clinical drug interaction studies in which venlafaxine did not inhibit the metabolism of several CYP3A4 substrates, including alprazolam, diazepam, and terfenadine.

Indinavir

In a study of 9 healthy volunteers, venlafaxine administered under steady-state conditions at 150 mg/day resulted in a 28% decrease in the AUC of a single 800 mg oral dose of indinavir and a 36% decrease in indinavir Cmax. Indinavir did not affect the pharmacokinetics of venlafaxine and ODV. The clinical significance of this finding is unknown.

CYP1A2

Venlafaxine did not inhibit CYP1A2 in vitro. This finding was confirmed in vivo by a clinical drug interaction study in which venlafaxine did not inhibit the metabolism of caffeine, a CYP1A2 substrate.

CYP2C9

Venlafaxine did not inhibit CYP2C9 in vitro. In vivo, venlafaxine 75 mg by mouth every 12 hours did not alter the pharmacokinetics of a single 500 mg dose of tolbutamide or the CYP2C9 mediated formation of 4-hydroxy-tolbutamide.

CYP2C19

Venlafaxine did not inhibit the metabolism of diazepam which is partially metabolized by CYP2C19 (see Diazepamabove).

Monoamine Oxidase Inhibitors

See CONTRAINDICATIONS.

CNS-Active Drugs

The risk of using venlafaxine in combination with other CNS-active drugs has not been systematically evaluated (except in the case of those CNS-active drugs noted above). Consequently, caution is advised if the concomitant administration of venlafaxine and such drugs is required (see CONTRAINDICATIONSand WARNINGS).

Serotonergic Drugs

Based on the mechanism of action of SNRIs and SSRIs, including venlafaxine hydrochloride, and the potential for serotonin syndrome, caution is advised when venlafaxine is coadministered with other drugs that may affect the serotonergic neurotransmitter systems, such as triptans, lithium, opioids, amphetamines, or St. John’s Wort (see WARNINGS, Serotonin Syndrome). If concomitant treatment of venlafaxine tablets, USP with these drugs is clinically warranted, careful observation of the patient is advised, particularly during treatment initiation and dose increases (see CONTRAINDICATIONSand WARNINGS, Serotonin Syndrome). The concomitant use of venlafaxine tablets, USP with tryptophan supplements is not recommended (see CONTRAINDICATIONSand WARNINGS, Serotonin Syndrome).

Triptans

There have been rare postmarketing reports of serotonin syndrome with use of an SSRI and a triptan. If concomitant treatment of venlafaxine tablets, USP with a triptan is clinically warranted, careful observation of the patient is advised, particularly during treatment initiation and dose increases (see WARNINGS, Serotonin Syndrome).

Drug-Laboratory Test Interactions

False-positive urine immunoassay screening tests for phencyclidine (PCP) and amphetamine have been reported in patients taking venlafaxine. This is due to lack of specificity of the screening tests. False positive test results may be expected for several days following discontinuation of venlafaxine therapy. Confirmatory tests, such as gas chromatography/mass spectrometry, will distinguish venlafaxine from PCP and amphetamine.

Electroconvulsive Therapy

There are no clinical data establishing the benefit of electroconvulsive therapy combined with venlafaxine tablets, USP treatment.

Postmarketing Spontaneous Drug Interaction Reports

See ADVERSE REACTIONS, Postmarketing Reports.

Carcinogenesis, Mutagenesis, Impairment of Fertility

Carcinogenesis

Venlafaxine was given by oral gavage to mice for 18 months at doses up to 120 mg/kg per day, which was 16 times, on a mg/kg basis, and 1.7 times on a mg/m^2basis, the maximum recommended human dose. Venlafaxine was also given to rats by oral gavage for 24 months at doses up to 120 mg/kg per day. In rats receiving the 120 mg/kg dose, plasma levels of venlafaxine were 1 times (male rats) and 6 times (female rats) the plasma levels of patients receiving the maximum recommended human dose. Plasma levels of the O-desmethyl metabolite were lower in rats than in patients receiving the maximum recommended dose. Tumors were not increased by venlafaxine treatment in mice or rats.

Mutagenicity

Venlafaxine and the major human metabolite, O-desmethylvenlafaxine (ODV), were not mutagenic in the Ames reverse mutation assay in Salmonella bacteria or the CHO/HGPRT mammalian cell forward gene mutation assay. Venlafaxine was also not mutagenic in the in vitro BALB/c-3T3 mouse cell transformation assay, the sister chromatid exchange assay in cultured CHO cells, or the in vivo chromosomal aberration assay in rat bone marrow. ODV was not mutagenic in the in vitro CHO cell chromosomal aberration assay. There was a clastogenic response in the in vivo chromosomal aberration assay in rat bone marrow in male rats receiving 200 times, on a mg/kg basis, or 50 times, on a mg/m^2 basis, the maximum human daily dose. The no effect dose was 67 times (mg/kg) or 17 times (mg/m^2) the human dose.

Impairment of Fertility

Reproduction and fertility studies of venlafaxine in rats showed no adverse effects on male or female fertility at oral doses of up to 2 times the maximum recommended human dose of 225 mg/day on a mg/m^2 basis.

However, reduced fertility was observed in a study in which male and female rats were treated with O-desmethylvenlafaxine (ODV), the major human metabolite of venlafaxine, prior to and during mating and gestation. This occurred at an ODV exposure (AUC) approximately 2 to 3 times that associated with a human venlafaxine dose of 225 mg/day.

Pregnancy

Teratogenic Effects

Venlafaxine did not cause malformations in offspring of rats or rabbits given doses up to 11 times (rat) or 12 times (rabbit) the maximum recommended human daily dose on a mg/kg basis, or 2.5 times (rat) and 4 times (rabbit) the human daily dose on a mg/m^2basis. However, in rats, there was a decrease in pup weight, an increase in stillborn pups, and an increase in pup deaths during the first 5 days of lactation, when dosing began during pregnancy and continued until weaning. The cause of these deaths is not known. These effects occurred at 10 times (mg/kg) or 2.5 times (mg/m^2) the maximum human daily dose. The no effect dose for rat pup mortality was 1.4 times the human dose on a mg/kg basis or 0.25 times the human dose on a mg/m^2basis. There are no adequate and well-controlled studies in pregnant women. Because animal reproduction studies are not always predictive of human response, this drug should be used during pregnancy only if clearly needed.

Non-teratogenic Effects
Based on data from published observational studies, exposure to SSRIs, particularly in the month before delivery, has been associated with a less than 2-fold increase in the risk of postpartum hemorrhage (see PRECAUTIONS: Abnormal Bleeding).

Neonates exposed to venlafaxine tablets, USP, other SNRIs (Serotonin and Norepinephrine Reuptake Inhibitors), or SSRIs (Selective Serotonin Reuptake Inhibitors), late in the third trimester have developed complications requiring prolonged hospitalization, respiratory support, and tube feeding. Such complications can arise immediately upon delivery. Reported clinical findings have included respiratory distress, cyanosis, apnea, seizures, temperature instability, feeding difficulty, vomiting, hypoglycemia, hypotonia, hypertonia, hyperreflexia, tremor, jitteriness, irritability, and constant crying. These features are consistent with either a direct toxic effect of SSRIs and SNRIs or, possibly, a drug discontinuation syndrome. It should be noted that, in some cases, the clinical picture is consistent with serotonin syndrome (see PRECAUTIONS, Drug Interactions, CNS-Active Drugs). When treating a pregnant woman with venlafaxine tablets, USP during the third trimester, the physician should carefully consider the potential risks and benefits of treatment (see DOSAGE AND ADMINISTRATION).

Maternal Adverse Reactions
Use of venlafaxine tablets, USP in the month before delivery may be associated with an increased risk of postpartum hemorrhage (see PRECAUTIONS: Abnormal Bleeding).

Labor and Delivery

The effect of venlafaxine tablets, USP on labor and delivery in humans is unknown.

Nursing Mothers

Venlafaxine and ODV have been reported to be excreted in human milk. Because of the potential for serious adverse reactions in nursing infants from venlafaxine tablets, USP, a decision should be made whether to discontinue nursing or to discontinue the drug, taking into account the importance of the drug to the mother.

Pediatric Use

Safety and effectiveness in the pediatric population have not been established (see BOX WARNINGand WARNINGS, Clinical Worsening and Suicide Risk). Two placebo-controlled trials in 766 pediatric patients with MDD and two placebo-controlled trials in 793 pediatric patients with GAD have been conducted with venlafaxine hydrochloride extended-release capsules, and the data were not sufficient to support a claim for use in pediatric patients.

Anyone considering the use of venlafaxine tablets, USP in a child or adolescent must balance the potential risks with the clinical need.

Although no studies have been designed to primarily assess venlafaxine hydrochloride extended-release capsule's impact on the growth, development, and maturation of children and adolescents, the studies that have been done suggest that venlafaxine hydrochloride extended-release capsules may adversely affect weight and height (see PRECAUTIONS, General, Changes in Height and Changes in Weight). Should the decision be made to treat a pediatric patient with venlafaxine tablets, USP, regular monitoring of weight and height is recommended during treatment, particularly if it is to be continued long term. The safety of venlafaxine hydrochloride extended-release capsule treatment for pediatric patients has not been systematically assessed for chronic treatment longer than six months in duration.

In the studies conducted in pediatric patients (ages 6 to 17), the occurrence of blood pressure and cholesterol increases considered to be clinically relevant in pediatric patients was similar to that observed in adult patients. Consequently, the precautions for adults apply to pediatric patients (see WARNINGS, Sustained Hypertensionand PRECAUTIONS, General, Serum Cholesterol Elevation).

Geriatric Use

Of the 2,897 patients in Phase 2 and Phase 3 depression studies with venlafaxine tablets, USP, 12% (357) were 65 years of age or over. No overall differences in effectiveness or safety were observed between these patients and younger patients, and other reported clinical experience generally has not identified differences in response between the elderly and younger patients. However, greater sensitivity of some older individuals cannot be ruled out. SSRIs and SNRIs, including venlafaxine tablets, USP, have been associated with cases of clinically significant hyponatremia in elderly patients, who may be at greater risk for this adverse event (see PRECAUTIONS, Hyponatremia).

The pharmacokinetics of venlafaxine and ODV are not substantially altered in the elderly (see CLINICAL PHARMACOLOGY). No dose adjustment is recommended for the elderly on the basis of age alone, although other clinical circumstances, some of which may be more common in the elderly, such as renal or hepatic impairment, may warrant a dose reduction (see DOSAGE AND ADMINISTRATION).

ADVERSE REACTIONS

Associated With Discontinuation of Treatment

Nineteen percent (537/2897) of venlafaxine patients in Phase 2 and Phase 3 depression studies discontinued treatment due to an adverse event. The more common events (≥1%) associated with discontinuation and considered to be drug-related (i.e., those events associated with dropout at a rate approximately twice or greater for venlafaxine compared to placebo) included:

 | Venlafaxine | Placebo
CNS
Somnolence | 3% | 1%
Insomnia | 3% | 1%
Dizziness | 3% | -
Nervousness | 2% | -
Dry mouth | 2% | -
Anxiety | 2% | 1%
Gastrointestinal
Nausea | 6% | 1%
Urogenital
Abnormal ejaculation* | 3% | -
Other
Headache | 3% | 1%
Asthenia | 2% | -
Sweating | 2% | -

* Percentages based on the number of males.

- Less than 1%

Incidence in Controlled Trials

Commonly Observed Adverse Events in Controlled Clinical Trials

The most commonly observed adverse events associated with the use of venlafaxine tablets, USP (incidence of 5% or greater) and not seen at an equivalent incidence among placebo-treated patients (i.e., incidence for venlafaxine tablets, USP at least twice that for placebo), derived from the 1% incidence table below, were asthenia, sweating, nausea, constipation, anorexia, vomiting, somnolence, dry mouth, dizziness, nervousness, anxiety, tremor, and blurred vision as well as abnormal ejaculation/orgasm and impotence in men.

Adverse Events Occurring at an Incidence of 1% or More Among Venlafaxine tablets, USP-Treated Patients

The table that follows enumerates adverse events that occurred at an incidence of 1% or more, and were more frequent than in the placebo group, among venlafaxine tablets, USP-treated patients who participated in short-term (4 to 8 week) placebo-controlled trials in which patients were administered doses in a range of 75 to 375 mg/day. This table shows the percentage of patients in each group who had at least one episode of an event at some time during their treatment. Reported adverse events were classified using a standard COSTART-based Dictionary terminology.

The prescriber should be aware that these figures cannot be used to predict the incidence of side effects in the course of usual medical practice where patient characteristics and other factors differ from those which prevailed in the clinical trials. Similarly, the cited frequencies cannot be compared with figures obtained from other clinical investigations involving different treatments, uses and investigators. The cited figures, however, do provide the prescribing physician with some basis for estimating the relative contribution of drug and nondrug factors to the side effect incidence rate in the population studied.

TABLE 2: Treatment-Emergent Adverse Experience Incidence in 4 to 8 Week Placebo-Controlled Clinical Trials^1

Body System | Preferred Term | Venlafaxine tablets, USP; (n=1033) | Placebo; (n=609)
Body as a Whole | Headache | 25% | 24%
 | Asthenia | 12% | 6%
 | Infection | 6% | 5%
 | Chills | 3% | -
 | Chest pain | 2% | 1%
 | Trauma | 2% | 1%
Cardiovascular | Vasodilatation | 4% | 3%
 | Increased blood pressure/ hypertension | 2% | -
 | Tachycardia | 2% | -
 | Postural hypotension | 1% | -
Dermatological | Sweating | 12% | 3%
 | Rash | 3 % | 2%
 | Pruritus | 1% | -
Gastrointestinal | Nausea | 37% | 11%
 | Constipation | 15% | 7%
 | Anorexia | 11% | 2%
 | Diarrhea | 8% | 7%
 | Vomiting | 6% | 2%
 | Dyspepsia | 5% | 4%
 | Flatulence | 3% | 2%
Metabolic | Weight loss | 1% | -
Nervous System | Somnolence | 23% | 9%
 | Dry mouth | 22% | 11%
 | Dizziness | 19% | 7%
 | Insomnia | 18% | 10%
 | Nervousness | 13% | 6%
 | Anxiety | 6% | 3%
 | Tremor | 5% | 1%
 | Abnormal dreams | 4% | 3%
 | Hypertonia | 3% | 2%
 | Paresthesia | 3% | 2%
 | Libido decreased | 2% | -
 | Agitation | 2% | -
 | Confusion | 2% | 1%
 | Thinking abnormal | 2% | 1%
 | Depersonalization | 1% | -
 | Depression | 1% | -
 | Urinary retention | 1% | -
 | Twitching | 1% | -
Respiration | Yawn | 3% | -
Special Senses | Blurred vision | 6% | 2%
 | Taste perversion | 2% | -
 | Tinnitus | 2% | -
 | Mydriasis | 2% | -
Urogenital System | Abnormal ejaculation/orgasm | 12%^2 | -^2
 | Impotence | 6%^2 | -^2
 | Urinary frequency | 3% | 2%
 | Urination impaired | 2% | -
 | Orgasm disturbance | 2%^3 | -^3

^1Events reported by at least 1% of patients treated with venlafaxine tablets, USP are included, and are rounded to the nearest %. Events for which the venlafaxine tablets, USP incidence was equal to or less than placebo are not listed in the table, but included the following: abdominal pain, pain, back pain, flu syndrome, fever, palpitation, increased appetite, myalgia, arthralgia, amnesia, hypesthesia, rhinitis, pharyngitis, sinusitis, cough increased, and dysmenorrhea^3.

— Incidence less than 1%.

^2 Incidence based on number of male patients.

^3 Incidence based on number of female patients.

Dose Dependency of Adverse Events

A comparison of adverse event rates in a fixed-dose study comparing venlafaxine tablets, USP 75, 225, and 375 mg/day with placebo revealed a dose dependency for some of the more common adverse events associated with venlafaxine tablets, USP use, as shown in the table that follows. The rule for including events was to enumerate those that occurred at an incidence of 5% or more for at least one of the venlafaxine groups and for which the incidence was at least twice the placebo incidence for at least one venlafaxine tablets, USP group. Tests for potential dose relationships for these events (Cochran-Armitage Test, with a criterion of exact 2 sided p-value ≤0.05) suggested a dose-dependency for several adverse events in this list, including chills, hypertension, anorexia, nausea, agitation, dizziness, somnolence, tremor, yawning, sweating, and abnormal ejaculation.

TABLE 3: Treatment-Emergent Adverse Experience Incidence in a Dose Comparison Trial

 |  | Venlafaxine Tablets, USP (mg/day)
Body System/Preferred Term | Placebo(n=92) | 75 (n=89) | 225(n=89) | 375(n=88)
Body as a Whole
Abdominal pain | 3.3% | 3.4% | 2.2% | 8.0%
Asthenia | 3.3% | 16.9% | 14.6% | 14.8%
Chills | 1.1% | 2.2% | 5.6% | 6.8%
Infection | 2.2% | 2.2% | 5.6% | 2.3%
Cardiovascular System
Hypertension | 1.1% | 1.1% | 2.2% | 4.5%
Vasodilatation | 0.0% | 4.5% | 5.6% | 2.3%
Digestive System
Anorexia | 2.2% | 14.6% | 13.5% | 17.0%
Dyspepsia | 2.2% | 6.7% | 6.7% | 4.5%
Nausea | 14.1% | 32.6% | 38.2% | 58.0%
Vomiting | 1.1% | 7.9% | 3.4% | 6.8%
Nervous System
Agitation | 0.0% | 1.1% | 2.2% | 4.5%
Anxiety | 4.3% | 11.2% | 4.5% | 2.3%
Dizziness | 4.3% | 19.1% | 22.5% | 23.9%
Insomnia | 9.8% | 22.5% | 20.2% | 13.6%
Libido decreased | 1.1% | 2.2% | 1.1% | 5.7%
Nervousness | 4.3% | 21.3% | 13.5% | 12.5%
Somnolence | 4.3% | 16.9% | 18.0% | 26.1%
Tremor | 0.0% | 1.1% | 2.2% | 10.2%
Respiratory System
Yawn | 0.0% | 4.5% | 5.6% | 8.0%
Skin and Appendages
Sweating | 5.4% | 6.7% | 12.4% | 19.3%
Special Senses
Abnormality of accommodation | 0.0% | 9.1% | 7.9% | 5.6%
Urogenital System
Abnormal ejaculation/orgasm | 0.0% | 4.5% | 2.2% | 12.5%
Impotence | 0.0% | 5.8% | 2.1% | 3.6%
(Number of men) | (n=63) | (n=52) | (n=48) | (n=56)

Adaptation to Certain Adverse Events

Over a 6 week period, there was evidence of adaptation to some adverse events with continued therapy (e.g., dizziness and nausea), but less to other effects (e.g., abnormal ejaculation and dry mouth).

Vital Sign Changes

Venlafaxine tablets, USP treatment (averaged over all dose groups) in clinical trials was associated with a mean increase in pulse rate of approximately 3 beats per minute, compared to no change for placebo. In a flexible-dose study, with doses in the range of 200 to 375 mg/day and mean dose greater than 300 mg/day, the mean pulse was increased by about 2 beats per minute compared with a decrease of about 1 beat per minute for placebo.

In controlled clinical trials, venlafaxine tablets, USP was associated with mean increases in diastolic blood pressure ranging from 0.7 to 2.5 mm Hg averaged over all dose groups, compared to mean decreases ranging from 0.9 to 3.8 mm Hg for placebo. However, there is a dose dependency for blood pressure increase (see WARNINGS).

Laboratory Changes

Of the serum chemistry and hematology parameters monitored during clinical trials with venlafaxine tablets, USP, a statistically significant difference with placebo was seen only for serum cholesterol. In premarketing trials, treatment with venlafaxine tablets, USP was associated with a mean final on-therapy increase in total cholesterol of 3 mg/dL.

Patients treated with venlafaxine tablets, USP for at least 3 months in placebo-controlled 12 month extension trials had a mean final on-therapy increase in total cholesterol of 9.1 mg/dL compared with a decrease of 7.1 mg/dL among placebo-treated patients. This increase was duration dependent over the study period and tended to be greater with higher doses. Clinically relevant increases in serum cholesterol, defined as 1) a final on-therapy increase in serum cholesterol ≥ 50 mg/dL from baseline and to a value ≥ 261 mg/dL or 2) an average on-therapy increase in serum cholesterol ≥ 50 mg/dL from baseline and to a value ≥ 261 mg/dL, were recorded in 5.3% of venlafaxine-treated patients and 0.0% of placebo-treated patients (see PRECAUTIONS, General, Serum Cholesterol Elevation).

ECG Changes

In an analysis of ECGs obtained in 769 patients treated with venlafaxine tablets, USP and 450 patients treated with placebo in controlled clinical trials, the only statistically significant difference observed was for heart rate, i.e., a mean increase from baseline of 4 beats per minute for venlafaxine tablets, USP. In a flexible-dose study, with doses in the range of 200 to 375 mg/day and mean dose greater than 300 mg/day, the mean change in heart rate was 8.5 beats per minute compared with 1.7 beats per minute for placebo (see PRECAUTIONS, General, Use in Patients With Concomitant Illness).

Other Events Observed During the Premarketing Evaluation of Venlafaxine
During its premarketing assessment, multiple doses of venlafaxine tablets, USP were administered to 2897 patients in Phase 2 and Phase 3 studies. In addition, in premarketing assessment of venlafaxine hydrochloride extended-release capsules, multiple doses were administered to 705 patients in Phase 3 major depressive disorder studies and venlafaxine tablets, USP was administered to 96 patients. During its premarketing assessment, multiple doses of venlafaxine hydrochloride extended-release capsules were also administered to 1381 patients in Phase 3 GAD studies and 277 patients in Phase 3 Social Anxiety Disorder studies. The conditions and duration of exposure to venlafaxine in both development programs varied greatly, and included (in overlapping categories) open and double-blind studies, uncontrolled and controlled studies, inpatient (venlafaxine tablets, USP only) and outpatient studies, fixed-dose and titration studies. Untoward events associated with this exposure were recorded by clinical investigators using terminology of their own choosing. Consequently, it is not possible to provide a meaningful estimate of the proportion of individuals experiencing adverse events without first grouping similar types of untoward events into a smaller number of standardized event categories.

In the tabulations that follow, reported adverse events were classified using a standard COSTART-based Dictionary terminology. The frequencies presented, therefore, represent the proportion of the 5356 patients exposed to multiple doses of either formulation of venlafaxine who experienced an event of the type cited on at least one occasion while receiving venlafaxine. All reported events are included except those already listed in Table 2 and those events for which a drug cause was remote. If the COSTART term for an event was so general as to be uninformative, it was replaced with a more informative term. It is important to emphasize that, although the events reported occurred during treatment with venlafaxine, they were not necessarily caused by it.

Events are further categorized by body system and listed in order of decreasing frequency using the following definitions: frequent adverse events are defined as those occurring on one or more occasions in at least 1/100 patients; infrequent adverse events are those occurring in 1/100 to 1/1000 patients; rare events are those occurring in fewer than 1/1000 patients.

Body as a whole— Frequent:accidental injury, chest pain substernal, neck pain; Infrequent:face edema, intentional injury, malaise, moniliasis, neck rigidity, pelvic pain, photosensitivity reaction, suicide attempt, withdrawal syndrome; Rare:appendicitis, bacteremia, carcinoma, cellulitis.

Cardiovascular system— Frequent:migraine; Infrequent:angina pectoris, arrhythmia, extrasystoles, hypotension, peripheral vascular disorder (mainly cold feet and/or cold hands), syncope, thrombophlebitis; Rare:aortic aneurysm, arteritis, first-degree atrioventricular block, bigeminy, bradycardia, bundle branch block, capillary fragility, cardiovascular disorder (mitral valve and circulatory disturbance), cerebral ischemia, coronary artery disease, congestive heart failure, heart arrest, mucocutaneous hemorrhage, myocardial infarct, pallor.

Digestive system— Frequent:eructation; Infrequent:bruxism, colitis, dysphagia, tongue edema, esophagitis, gastritis, gastroenteritis, gastrointestinal ulcer, gingivitis, glossitis, rectal hemorrhage, hemorrhoids, melena, oral moniliasis, stomatitis, mouth ulceration; Rare:cheilitis, cholecystitis, cholelithiasis, duodenitis, esophageal spasm, hematemesis, gastrointestinal hemorrhage, gum hemorrhage, hepatitis, ileitis, jaundice, intestinal obstruction, parotitis, periodontitis, proctitis, increased salivation, soft stools, tongue discoloration.

Endocrine system— Rare:goiter, hyperthyroidism, hypothyroidism, thyroid nodule, thyroiditis.

Hemic and lymphatic system— Frequent:ecchymosis; Infrequent:anemia, leukocytosis, leukopenia, lymphadenopathy, thrombocythemia, thrombocytopenia; Rare:basophilia, bleeding time increased, cyanosis, eosinophilia, lymphocytosis, multiple myeloma, purpura.

Metabolic and nutritional— Frequent:edema, weight gain; Infrequent:alkaline phosphatase increased, dehydration, hypercholesteremia, hyperglycemia, hyperlipemia, hypokalemia, SGOT (AST) increased, SGPT (ALT) increased, thirst; Rare:alcohol intolerance, bilirubinemia, BUN increased, creatinine increased, diabetes mellitus, glycosuria, gout, healing abnormal, hemochromatosis, hypercalcinuria, hyperkalemia, hyperphosphatemia, hyperuricemia, hypocholesteremia, hypoglycemia, hyponatremia, hypophosphatemia, hypoproteinemia, uremia.

Musculoskeletal system— Infrequent:arthritis, arthrosis, bone pain, bone spurs, bursitis, leg cramps, myasthenia, tenosynovitis; Rare:pathological fracture, myopathy, osteoporosis, osteosclerosis, plantar fasciitis, rheumatoid arthritis, tendon rupture.

Nervous system— Frequent:trismus, vertigo; Infrequent:akathisia, apathy, ataxia, circumoral paresthesia, CNS stimulation, emotional lability, euphoria, hallucinations, hostility, hyperesthesia, hyperkinesia, hypotonia, incoordination, libido increased, manic reaction, myoclonus, neuralgia, neuropathy, psychosis, seizure, abnormal speech, stupor; Rare:akinesia, alcohol abuse, aphasia, bradykinesia, buccoglossal syndrome, cerebrovascular accident, loss of consciousness, delusions, dementia, dystonia, facial paralysis, feeling drunk, abnormal gait, Guillain-Barre Syndrome, hyperchlorhydria, hypokinesia, impulse control difficulties, neuritis, nystagmus, paranoid reaction, paresis, psychotic depression, reflexes decreased, reflexes increased, suicidal ideation, torticollis.

Respiratory system— Frequent:bronchitis, dyspnea; Infrequent:asthma, chest congestion, epistaxis, hyperventilation, laryngismus, laryngitis, pneumonia, voice alteration; Rare:atelectasis, hemoptysis, hypoventilation, hypoxia, larynx edema, pleurisy, pulmonary embolus, sleep apnea.

Skin and appendages— Infrequent:acne, alopecia, brittle nails, contact dermatitis, dry skin, eczema, skin hypertrophy, maculopapular rash, psoriasis, urticaria; Rare:erythema nodosum, exfoliative dermatitis, lichenoid dermatitis, hair discoloration, skin discoloration, furunculosis, hirsutism, leukoderma, petechial rash, pustular rash, vesiculobullous rash, seborrhea, skin atrophy, skin striae.

Special senses— Frequent:abnormality of accommodation, abnormal vision; Infrequent:cataract, conjunctivitis, corneal lesion, diplopia, dry eyes, eye pain, hyperacusis, otitis media, parosmia, photophobia, taste loss, visual field defect; Rare:blepharitis, chromatopsia, conjunctival edema, deafness, exophthalmos, angle-closure glaucoma, retinal hemorrhage, subconjunctival hemorrhage, keratitis, labyrinthitis, miosis, papilledema, decreased pupillary reflex, otitis externa, scleritis, uveitis.

Urogenital system— Frequent:metrorrhagia*, prostatic disorder (prostatitis and enlarged prostate)*, vaginitis*; Infrequent:albuminuria, amenorrhea*, cystitis, dysuria, hematuria, leukorrhea*, menorrhagia*, nocturia, bladder pain, breast pain, polyuria, pyuria, urinary incontinence, urinary urgency, vaginal hemorrhage*; Rare:abortion*, anuria, balanitis*, breast discharge, breast engorgement, breast enlargement, endometriosis*, fibrocystic breast, calcium crystalluria, cervicitis*, ovarian cyst*, prolonged erection*, gynecomastia (male)*, hypomenorrhea*, kidney calculus, kidney pain, kidney function abnormal, female lactation*, mastitis, menopause*, oliguria, orchitis*, pyelonephritis, salpingitis*, urolithiasis, uterine hemorrhage*, uterine spasm*, vaginal dryness*.

* Based on the number of men and women as appropriate.

Postmarketing Reports

Voluntary reports of other adverse events temporally associated with the use of venlafaxine that have been received since market introduction and that may have no causal relationship with the use of venlafaxine include the following: agranulocytosis, anaphylaxis, anosmia, angioedema, aplastic anemia, catatonia, congenital anomalies, impaired coordination and balance, CPK increased, deep vein thrombophlebitis, delirium, EKG abnormalities such as QT prolongation; cardiac arrhythmias including atrial fibrillation, supraventricular tachycardia, ventricular extrasystole, and rare reports of ventricular fibrillation and ventricular tachycardia, including torsade de pointes; toxic epidermal necrolysis/Stevens-Johnson syndrome, erythema multiforme, extrapyramidal symptoms (including dyskinesia and tardive dyskinesia), angle-closure glaucoma, hemorrhage (including eye and gastrointestinal bleeding), hyposmia, hepatic events (including GGT elevation; abnormalities of unspecified liver function tests; liver damage, necrosis, or failure; and fatty liver), interstitial lung disease, involuntary movements, LDH increased, neutropenia, night sweats, pancreatitis, pancytopenia, panic, prolactin increased, renal failure, rhabdomyolysis, shock-like electrical sensations or tinnitus (in some cases, subsequent to the discontinuation of venlafaxine or tapering of dose), and syndrome of inappropriate antidiuretic hormone secretion (usually in the elderly).

There have been reports of elevated clozapine levels that were temporally associated with adverse events, including seizures, following the addition of venlafaxine. There have been reports of increases in prothrombin time, partial thromboplastin time, or INR when venlafaxine was given to patients receiving warfarin therapy.

DRUG ABUSE AND DEPENDENCE

Controlled Substance Class

Venlafaxine tablets, USP is not a controlled substance.

Physical and Psychological Dependence

In vitro studies revealed that venlafaxine has virtually no affinity for opiate, benzodiazepine, phencyclidine (PCP), or N-methyl-D-aspartic acid (NMDA) receptors.

Venlafaxine was not found to have any significant CNS stimulant activity in rodents. In primate drug discrimination studies, venlafaxine showed no significant stimulant or depressant abuse liability.

Discontinuation effects have been reported in patients receiving venlafaxine (see DOSAGE AND ADMINISTRATION).

While venlafaxine tablets, USP has not been systematically studied in clinical trials for its potential for abuse, there was no indication of drug-seeking behavior in the clinical trials. However, it is not possible to predict on the basis of premarketing experience the extent to which a CNS active drug will be misused, diverted, and/or abused once marketed. Consequently, physicians should carefully evaluate patients for history of drug abuse and follow such patients closely, observing them for signs of misuse or abuse of venlafaxine tablets, USP (e.g., development of tolerance, incrementation of dose, drug-seeking behavior).

OVERDOSAGE

Human Experience

There were 14 reports of acute overdose with venlafaxine tablets, USP, either alone or in combination with other drugs and/or alcohol, among the patients included in the premarketing evaluation. The majority of the reports involved ingestions in which the total dose of venlafaxine tablets, USP taken was estimated to be no more than several-fold higher than the usual therapeutic dose. The 3 patients who took the highest doses were estimated to have ingested approximately 6.75 g, 2.75 g, and 2.5 g. The resultant peak plasma levels of venlafaxine for the latter 2 patients were 6.24 and 2.35 mcg/mL, respectively, and the peak plasma levels of O-desmethylvenlafaxine were 3.37 and 1.30 mcg/mL, respectively. Plasma venlafaxine levels were not obtained for the patient who ingested 6.75 g of venlafaxine. All 14 patients recovered without sequelae. Most patients reported no symptoms. Among the remaining patients, somnolence was the most commonly reported symptom. The patient who ingested 2.75 g of venlafaxine was observed to have 2 generalized convulsions and a prolongation of QTcto 500 msec, compared with 405 msec at baseline. Mild sinus tachycardia was reported in 2 of the other patients.

In postmarketing experience, overdose with venlafaxine has occurred predominantly in combination with alcohol and/or other drugs. The most commonly reported events in overdosage include tachycardia, changes in level of consciousness (ranging from somnolence to coma), mydriasis, seizures, and vomiting. Electrocardiogram changes (e.g., prolongation of QT interval, bundle branch block, QRS prolongation), ventricular tachycardia, bradycardia, hypotension, rhabdomyolysis, vertigo, liver necrosis, serotonin syndrome, and death have been reported.

Published retrospective studies report that venlafaxine overdosage may be associated with an increased risk of fatal outcomes compared to that observed with SSRI antidepressant products, but lower than that for tricyclic antidepressants. Epidemiological studies have shown that venlafaxine-treated patients have a higher preexisting burden of suicide risk factors than SSRI-treated patients. The extent to which the finding of an increased risk of fatal outcomes can be attributed to the toxicity of venlafaxine in overdosage as opposed to some characteristic(s) of venlafaxine-treated patients is not clear. Prescriptions for venlafaxine tablets, USP should be written for the smallest quantity of tablets consistent with good patient management, in order to reduce the risk of overdose.

Management of Overdosage

Treatment should consist of those general measures employed in the management of overdosage with any antidepressant.

Ensure an adequate airway, oxygenation, and ventilation. Monitor cardiac rhythm and vital signs. General supportive and symptomatic measures are also recommended. Induction of emesis is not recommended. Gastric lavage with a large-bore orogastric tube with appropriate airway protection, if needed, may be indicated if performed soon after ingestion or in symptomatic patients. Activated charcoal should be administered. Due to the large volume of distribution of this drug, forced diuresis, dialysis, hemoperfusion and exchange transfusion are unlikely to be of benefit. No specific antidotes for venlafaxine are known.

In managing overdosage, consider the possibility of multiple drug involvement. The physician should consider contacting a poison control center for additional information on the treatment of any overdose. Telephone numbers for certified poison control centers are listed in the Physicians' Desk Reference (PDR).

DOSAGE AND ADMINISTRATION

Initial Treatment

The recommended starting dose for venlafaxine tablets, USP is 75 mg/day, administered in two or three divided doses, taken with food. Depending on tolerability and the need for further clinical effect, the dose may be increased to 150 mg/day. If needed, the dose should be further increased up to 225 mg/day. When increasing the dose, increments of up to 75 mg/day should be made at intervals of no less than 4 days. In outpatient settings there was no evidence of usefulness of doses greater than 225 mg/day for moderately depressed patients, but more severely depressed inpatients responded to a mean dose of 350 mg/day. Certain patients, including more severely depressed patients, may therefore respond more to higher doses, up to a maximum of 375 mg/day, generally in three divided doses (see PRECAUTIONS, General, Use in Patients With Concomitant Illness).

Special Populations

Treatment of Pregnant Women During the Third Trimester

Neonates exposed to venlafaxine tablets, USP, other SNRIs, or SSRIs, late in the third trimester have developed complications requiring prolonged hospitalization, respiratory support, and tube feeding (see PRECAUTIONS). When treating pregnant women with venlafaxine tablets, USP during the third trimester, the physician should carefully consider the potential risks and benefits of treatment.

Dosage for Patients With Hepatic Impairment

Given the decrease in clearance and increase in elimination half-life for both venlafaxine and ODV that is observed in patients with hepatic cirrhosis and mild and moderate hepatic impairment compared to normal subjects (see CLINICAL PHARMACOLOGY), it is recommended that the total daily dose be reduced by 50% in patients with mild to moderate hepatic impairment. Since there was much individual variability in clearance between subjects with cirrhosis, it may be necessary to reduce the dose even more than 50%, and individualization of dosing may be desirable in some patients.

Dosage for Patients With Renal Impairment

Given the decrease in clearance for venlafaxine and the increase in elimination half-life for both venlafaxine and ODV that is observed in patients with renal impairment (GFR = 10 to 70 mL/min) compared to normals (see CLINICAL PHARMACOLOGY), it is recommended that the total daily dose be reduced by 25% in patients with mild to moderate renal impairment. It is recommended that the total daily dose be reduced by 50% in patients undergoing hemodialysis. Since there was much individual variability in clearance between patients with renal impairment, individualization of dosing may be desirable in some patients.

Dosage for Elderly Patients

No dose adjustment is recommended for elderly patients on the basis of age. As with any antidepressant, however, caution should be exercised in treating the elderly. When individualizing the dosage, extra care should be taken when increasing the dose.

Maintenance Treatment

It is generally agreed that acute episodes of major depressive disorder require several months or longer of sustained pharmacological therapy beyond response to the acute episode. In one study, in which patients responding during 8 weeks of acute treatment with venlafaxine hydrochloride extended-release capsules were assigned randomly to placebo or to the same dose of venlafaxine hydrochloride extended-release capsules (75, 150, or 225 mg/day, qAM) during 26 weeks of maintenance treatment as they had received during the acute stabilization phase, longer-term efficacy was demonstrated. A second longer-term study has demonstrated the efficacy of venlafaxine tablets, USP in maintaining an antidepressant response in patients with recurrent depression who had responded and continued to be improved during an initial 26 weeks of treatment and were then randomly assigned to placebo or venlafaxine tablets, USP for periods of up to 52 weeks on the same dose (100 to 200 mg/day, on a b.i.d. schedule) (see CLINICAL TRIALS). Based on these limited data, it is not known whether or not the dose of venlafaxine tablets, USP / venlafaxine hydrochloride extended-release capsules needed for maintenance treatment is identical to the dose needed to achieve an initial response. Patients should be periodically reassessed to determine the need for maintenance treatment and the appropriate dose for such treatment.

Discontinuing Venlafaxine Tablets, USP

Symptoms associated with discontinuation of venlafaxine tablets, USP, other SNRIs, and SSRIs, have been reported (see PRECAUTIONS). Patients should be monitored for these symptoms when discontinuing treatment. A gradual reduction in the dose rather than abrupt cessation is recommended whenever possible. If intolerable symptoms occur following a decrease in the dose or upon discontinuation of treatment, then resuming the previously prescribed dose may be considered. Subsequently, the physician may continue decreasing the dose but at a more gradual rate.

Switching a Patient To or From a Monoamine Oxidase Inhibitor (MAOI) Intended to Treat Psychiatric Disorders

At least 14 days should elapse between discontinuation of an MAOI intended to treat psychiatric disorders and initiation of therapy with venlafaxine tablets, USP. Conversely, at least 7 days should be allowed after stopping venlafaxine tablets, USP before starting an MAOI intended to treat psychiatric disorders (see CONTRAINDICATIONS).

Use of Venlafaxine Tablets, USP With Other MAOls, Such as Linezolid or Methylene Blue

Do not start venlafaxine tablets, USP in a patient who is being treated with linezolid or intravenous methylene blue because there is increased risk of serotonin syndrome. In a patient who requires more urgent treatment of a psychiatric condition, other interventions, including hospitalization, should be considered (see CONTRAINDICATIONS).

In some cases, a patient already receiving therapy with venlafaxine tablets, USP may require urgent treatment with linezolid or intravenous methylene blue. If acceptable alternatives to linezolid or intravenous methylene blue treatment are not available and the potential benefits of linezolid or intravenous methylene blue treatment are judged to outweigh the risks of serotonin syndrome in a particular patient, venlafaxine tablets, USP should be stopped promptly, and linezolid or intravenous methylene blue can be administered. The patient should be monitored for symptoms of serotonin syndrome for 7 days or until 24 hours after the last dose of linezolid or intravenous methylene blue, whichever comes first. Therapy with venlafaxine tablets, USP may be resumed 24 hours after the last dose of linezolid or intravenous methylene blue (see WARNINGS).

The risk of administering methylene blue by non-intravenous routes (such as oral tablets or by local injection) or in intravenous doses much lower than 1 mg/kg with venlafaxine tablets, USP is unclear. The clinician should, nevertheless, be aware of the possibility of emergent symptoms of serotonin syndrome with such use (see WARNINGS).

HOW SUPPLIED

Venlafaxine Tablets, USP 25 mg are peach colored, shield-shaped, uncoated, flat-faced beveled edge, tablets debossed with ‘392’ on one side and scored on the other side are available as follows:

Bottles of 100 NDC 57664-392-88

Venlafaxine Tablets, USP 37.5 mg are peach colored, shield-shaped, uncoated, flat-faced beveled edge, tablets debossed with ‘393’ on one side and scored on the other side are available as follows:

Bottles of 100 NDC 57664-393-88

Venlafaxine Tablets, USP 50 mg are peach colored, shield-shaped, uncoated, flat-faced beveled edge, tablets debossed with ‘394’ on one side and scored on the other side are available as follows:

Bottles of 100 NDC 57664-394-88

Venlafaxine Tablets, USP 75 mg are peach colored, shield-shaped, uncoated, flat-faced beveled edge, tablets debossed with ‘395’ on one side and scored on the other side are available as follows:

Bottles of 100 NDC 57664-395-88

Venlafaxine Tablets, USP 100 mg are peach colored, shield-shaped, uncoated, flat-faced beveled edge, tablets debossed with ‘396’ on one side and scored on the other side are available as follows:

Bottles of 100 NDC 57664-396-88

Store at 20° to 25°C (68° to 77°F) excursions permitted 15° to 30°C (59° to 86°F) [See USP Controlled Room Temperature].

Protect from light and moisture.

Manufactured by:

ALKALOIDA Chemical Company Zrt.

4440 Tiszavasvári

Kabay János u. 29.

Hungary

Distributed by:

Sun Pharmaceutical Industries, Inc.

Cranbury, NJ 08512

Revised: 08/2023

Medication Guide

Venlafaxine (ven-la-fax-een) Tablets, USP

Read the Medication Guide that comes with venlafaxine tablets, USP before you start taking it and each time you get a refill. There may be new information. This Medication Guide does not take the place of talking to your healthcare provider about your medical condition or treatment. Talk with your healthcare provider if there is something you do not understand or want to learn more about.

What is the most important information I should know about Venlafaxine Tablets, USP?

Venlafaxine tablets, USP and other antidepressant medicines may cause serious side effects, including:

1. Suicidal thoughts or actions:

• Venlafaxine tablets, USP and other antidepressant medicines may increase suicidal thoughts or actions in some children, teenagers, or young adults within the first few months of treatment or when the dose is changed. Depression or other serious mental illnesses are the most important causes of suicidal thoughts or actions.•Watch for these changes and call your healthcare provider right away if you notice:•New or sudden changes in mood, behavior, actions, thoughts, or feelings, especially if severe. •Pay particular attention to such changes when venlafaxine tablets, USPis started or when the dose is changed.

Keep all follow-up visits with your healthcare provider and call between visits if you are worried about symptoms.

Call your healthcare provider right away if you have any of the following symptoms, or call 911 if an emergency, especially if they are new, worse, or worry you:

•attempts to commit suicide•acting on dangerous impulses•acting aggressive or violent•thoughts about suicide or dying•new or worse depression•new or worse anxiety or panic attacks•feeling agitated, restless, angry or irritable•trouble sleeping•an increase in activity or talking more than what is normal for you•other unusual changes in behavior or mood

Call your healthcare provider right away if you have any of the following symptoms, or call 911 if an emergency. Venlafaxine Tablets, USP may be associated with these serious side effects:

2. Serotonin Syndrome

This condition can be life-threatening and may include:

•agitation, hallucinations, coma or other changes in mental status•coordination problems or muscle twitching (overactive reflexes)•racing heartbeat, high or low blood pressure•sweating or fever•nausea, vomiting, or diarrhea•muscle rigidity

3. Changes in blood pressure. Venlafaxine Tablets, USP may:

•increase your blood pressure. Control high blood pressure before starting treatment and monitor blood pressure regularly

4. Enlarged pupils (mydriasis).

5. Sexual problems (dysfunction).Taking serotonin and norepinephrine reuptake inhibitors (SNRIs), including venlafaxine tablets, USP, may cause sexual problems.

Symptoms in males may include:

•Delayed ejaculation or inability to have an ejaculation•Decreased sex drive•Problems getting or keeping an erection

Symptoms in females may include:

•Decreased sex drive•Delayed orgasm or inability to have an orgasm

Talk to your healthcare provider if you develop any changes in your sexual function or if you have any questions or concerns about sexual problems during treatment with venlafaxine tablets, USP. There may be treatments your healthcare provider can suggest.

6. Anxiety and insomnia.

7. Changes in appetite or weight.

•children and adolescents should have height and weight monitored during treatment

8. Manic/hypomanic episodes:

•greatly increased energy•severe trouble sleeping•racing thoughts•reckless behavior•unusually grand ideas•excessive happiness or irritability•talking more or faster than usual

9. Low salt (sodium) levels in the blood.

Elderly people may be at greater risk for this. Symptoms may include:

•headache•weakness or feeling unsteady•confusion, problems concentrating or thinking or memory problems

10. Seizures or convulsions.

11. Abnormal bleeding: venlafaxine tablets, USP and other antidepressant medicines may increase your risk of bleeding or bruising, especially if you take the blood thinner warfarin (Coumadin®, Jantoven®), a non-steroidal anti-inflammatory drug (NSAIDs, like ibuprofen or naproxen), or aspirin.

12. Elevated cholesterol.

13. Lung disease and pneumonia: venlafaxine tablets, USP may cause rare lung problems. Symptoms include:

•worsening shortness of breath•cough•chest discomfort

14. Severe allergic reactions:

•trouble breathing•swelling of the face, tongue, eyes or mouth•rash, itchy welts (hives) or blisters, alone or with fever or joint pain

15. Visual problems:

•eye pain•changes in vision•swelling or redness in or around the eye•Only some people are at risk for these problems. You may want to undergo an eye examination to see if you are at risk and receive preventative treatment if you are.

Do not stop Venlafaxine Tablets, USP without first talking to your healthcare provider. Stopping venlafaxine tablets, USP too quickly or changing from another antidepressant too quickly may cause serious symptoms including:

•anxiety, irritability

•feeling tired, restless or problems sleeping

•headache, sweating, dizziness

•electric shock-like sensations, shaking, confusion, nightmares

•vomiting, nausea, diarrhea

What is Venlafaxine Tablets, USP?

Venlafaxine tablets, USP is a prescription medicine used to treat depression. It is important to talk with your healthcare provider about the risks of treating depression and also the risks of not treating it. You should discuss all treatment choices with your healthcare provider.

Talk to your healthcare provider if you do not think that your condition is getting better with venlafaxine tablets, USP treatment.

Who should not take Venlafaxine Tablets, USP?

Do not take venlafaxine tablets, USP if you:

•are allergic to venlafaxine tablets, USP or any of the ingredients in venlafaxine tablets, USP. See the end of this Medication Guide for a complete list of ingredients in venlafaxine tablets, USP.

•have uncontrolled narrow-angle glaucoma

•take a Monoamine Oxidase Inhibitor (MAOI). Ask your healthcare provider or pharmacist if you are not sure if you take an MAOI, including the antibiotic linezolid.

•Do not take an MAOI within 7 days of stopping venlafaxine tablets, USP unless directed to do so by your physician.

•Do not start venlafaxine tablets, USP if you stopped taking an MAOI in the last 2 weeks unless directed to do so by your physician.

People who take Venlafaxine Tablets, USP close in time to an MAOI may have serious or even life-threatening side effects. Get medical help right away if you have any of these symptoms:

•high fever

•uncontrolled muscle spasms

•stiff muscles

•rapid changes in heart rate or blood pressure

•confusion

•loss of consciousness (pass out)

What should I tell my healthcare provider before taking Venlafaxine Tablets, USP? Ask if you are not sure.

Before starting venlafaxine tablets, USP, tell your healthcare provider if you:

- Are taking certain drugs such as:

• Amphetamines
• Medicines used to treat migraine headaches such as:
o triptans
• Medicines used to treat mood, anxiety, psychotic or thought disorders, such as:
o tricyclic antidepressants
o lithium
o SSRIs
o SNRIs
o antipsychotic drugs
• Medicines used to treat pain such as:
o tramadol

o meperidine
o methadone
o other opioids
• Medicines used to thin your blood such as:
o warfarin
• Medicines used to treat heartburn such as:
o Cimetidine
• Over-the-counter medicines or supplements such as:
o Aspirin or other NSAIDs
o Tryptophan
o St. John’s Wort

•have heart problems

•have diabetes

•have liver problems

•have kidney problems

•have thyroid problems

•have glaucoma

•have or had seizures or convulsions

•have bipolar disorder or mania

•have low sodium levels in your blood

•have high blood pressure

•have high cholesterol

•have or had bleeding problems

•are pregnant or plan to become pregnant. It is not known if venlafaxine tablets, USP will harm your unborn baby. Talk to your healthcare provider about the benefits and risks of treating depression during pregnancy

•are breast-feeding or plan to breast-feed. Some venlafaxine tablets, USP may pass into your breast milk. Talk to your healthcare provider about the best way to feed your baby while taking venlafaxine tablets, USP.

Tell your healthcare provider about all the medicines that you take, including prescription and non-prescription medicines, vitamins, and herbal supplements. Venlafaxine tablets, USP and some medicines may interact with each other, may not work as well, or may cause serious side effects.

Your healthcare provider or pharmacist can tell you if it is safe to take venlafaxine tablets, USP with your other medicines. Do not start or stop any medicine while taking venlafaxine tablets, USP without talking to your healthcare provider first.

If you take venlafaxine tablets, USP, you should not take any other medicines that contain (venlafaxine) including: venlafaxine HCl.

How should I take Venlafaxine Tablets, USP?

•Take venlafaxine tablets, USP exactly as prescribed. Your healthcare provider may need to change the dose of venlafaxine tablets, USP until it is the right dose for you.• Venlafaxine tablets, USP is to be taken with food.•If you miss a dose of venlafaxine tablets, USP, take the missed dose as soon as you remember. If it is almost time for the next dose, skip the missed dose and take your next dose at the regular time. Do not take two doses of venlafaxine tablets, USP at the same time.•If you take too much venlafaxine tablets, USP, call your healthcare provider or poison control center right away, or get emergency treatment.•When switching from another antidepressant to venlafaxine tablets, USP your doctor may want to lower the dose of the initial antidepressant first to avoid side effects.

What should I avoid while taking Venlafaxine Tablets, USP?
Venlafaxine tablets, USP can cause sleepiness or may affect your ability to make decisions, think clearly, or react quickly. You should not drive, operate heavy machinery, or do other dangerous activities until you know how venlafaxine tablets, USPaffects you. Do not drink alcohol while using venlafaxine tablets, USP.

What are the possible side effects of Venlafaxine Tablets, USP?

Venlafaxine tablets, USP may cause serious side effects, including:

•See "What is the most important information I should know about Venlafaxine Tablets, USP?"•Increased cholesterol- have your cholesterol checked regularly •Newborns whose mothers take venlafaxine tablets, USP in the third trimester may have problems right after birth including:•problems feeding and breathing•seizures•shaking, jitteriness or constant crying•Narrow-angle glaucoma/enlarged pupils. Check eye pressure regularly if you:•have a history of increased eye pressure•are at risk for certain types of glaucoma

Common possible side effects in people who take venlafaxine tablets, USP include:

•unusual dreams•sexual problems•loss of appetite, constipation, diarrhea, nausea or vomiting, or dry mouth•feeling tired, fatigued or overly sleepy•change in sleep habits, problems sleeping•yawning•tremor or shaking•dizziness, blurred vision•sweating•feeling anxious, nervous or jittery•headache•increase in heart rate

Tell your healthcare provider if you have any side effect that bothers you or that does not go away. These are not all the possible side effects of venlafaxine tablets, USP. For more information, ask your healthcare provider or pharmacist.

CALL YOUR DOCTOR FOR MEDICAL ADVICE ABOUT SIDE EFFECTS. YOU MAY REPORT SIDE EFFECTS TO THE FDA AT 1-800-FDA-1088.

How should I store Venlafaxine Tablets, USP?

• Store at 20° to 25°C (68° to 77°F) excursions permitted 15° to 30°C (59° to 86°F) [See USP Controlled Room Temperature].•Keep venlafaxine tablets, USP in a dry place.

Keep Venlafaxine Tablets, USP and all medicines out of the reach of children.

General information about venlafaxine tablets, USP. Medicines are sometimes prescribed for purposes other than those listed in a Medication Guide. Do not use venlafaxine tablets, USP for a condition for which it was not prescribed. Do not give venlafaxine tablets, USP to other people, even if they have same condition. It may harm them.

This Medication Guide summarizes the most important information about venlafaxine tablets, USP. If you would like more information, talk with your healthcare provider. You may ask your healthcare provider or pharmacist for information about venlafaxine tablets, USP that is written for healthcare professionals.

To report SUSPECTED ADVERSE REACTIONS, contact Sun Pharmaceutical Industries, Inc. at 1-800-818-4555.

What are the ingredients in Venlafaxine Tablets, USP?

Active ingredient: (venlafaxine)

Inactive ingredients:

• Tablets:microcrystalline cellulose, lactose monohydrate, pregelatinized starch, sodium starch glycolate, iron oxide red, iron oxide yellow, colloidal silicon dioxide, and magnesium stearate

This Medication Guide has been approved by the U.S. Food and Drug Administration for all antidepressants.

Manufactured by:

ALKALOIDA Chemical Company Zrt.

4440 Tiszavasvári

Kabay János u. 29.

Hungary

Distributed by:

Sun Pharmaceutical Industries, Inc.

Cranbury, NJ 08512

Revised: 05/2024

PACKAGE LABEL.PRINCIPAL DISPLAY PANEL

Venlafaxine Tablets, USP 25 mg

Venlafaxine Tablets, USP 37.5 mg

Venlafaxine Tablets, USP 50 mg

Venlafaxine Tablets, USP 75 mg

Venlafaxine Tablets, USP 100 mg